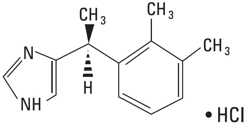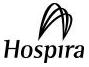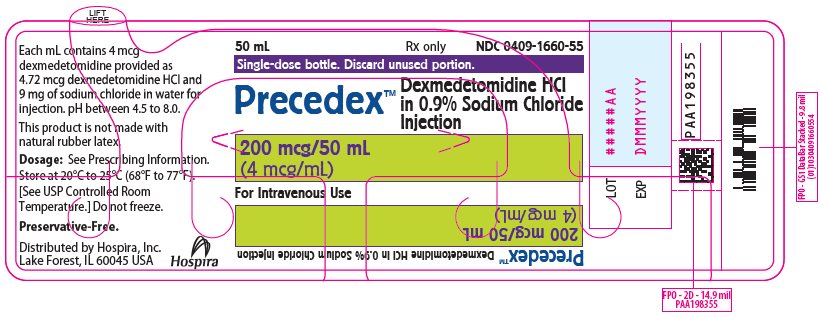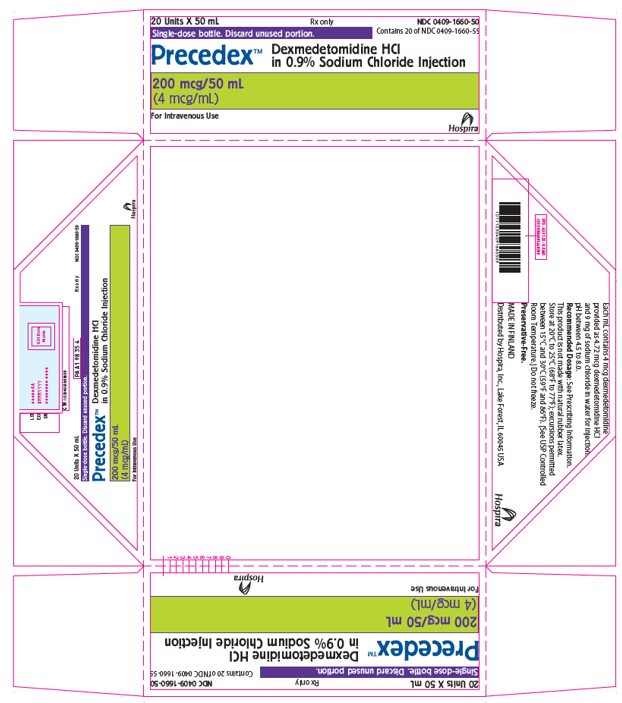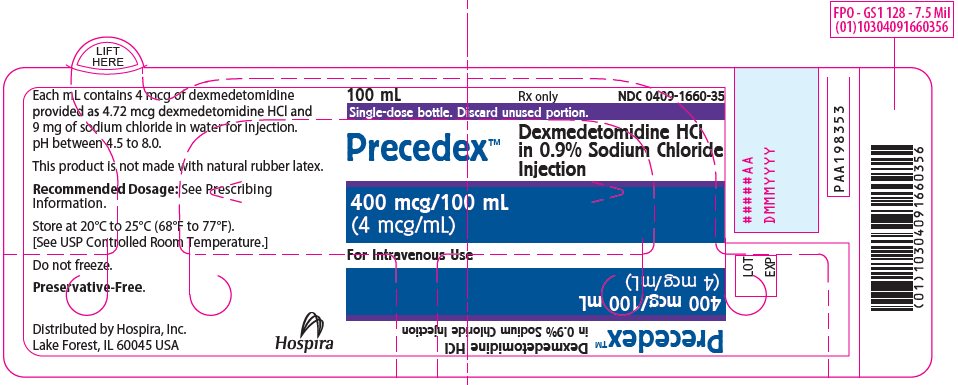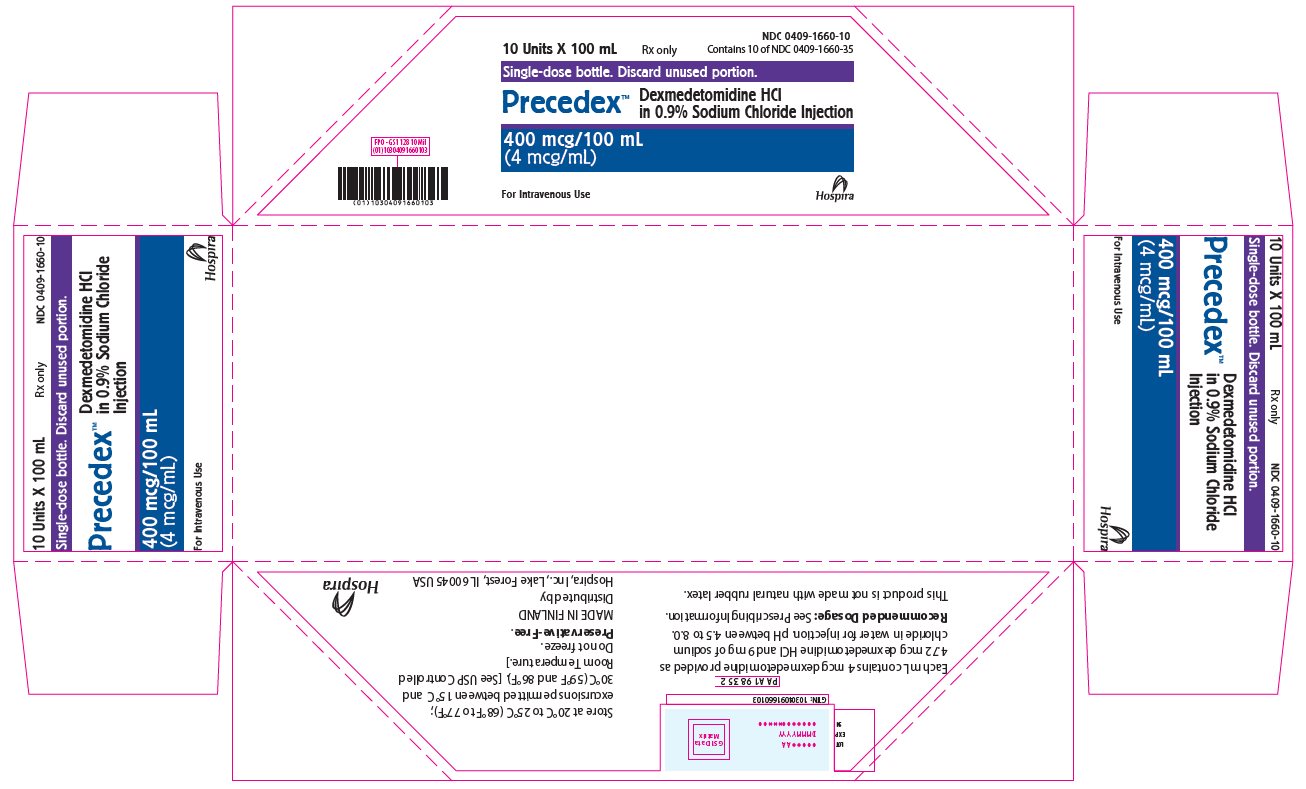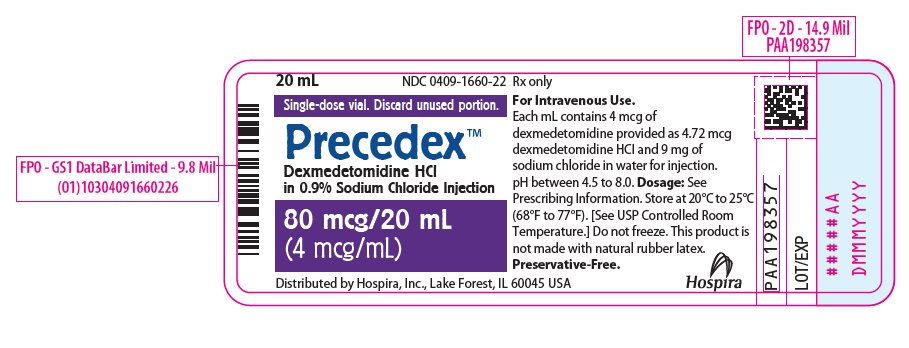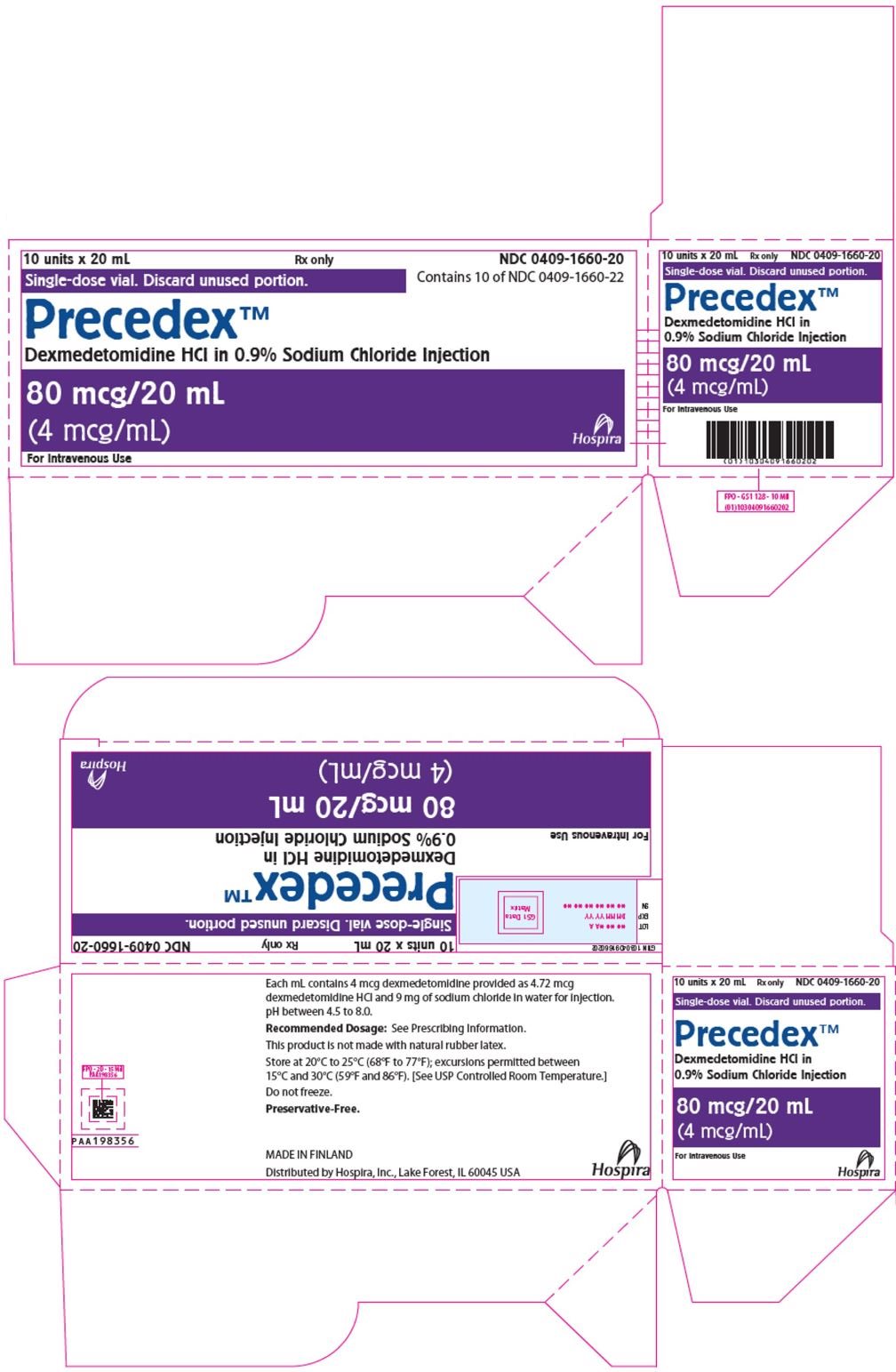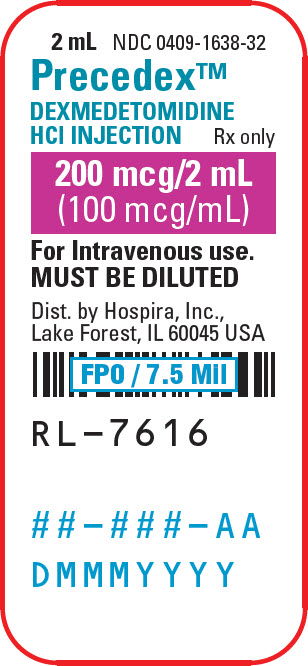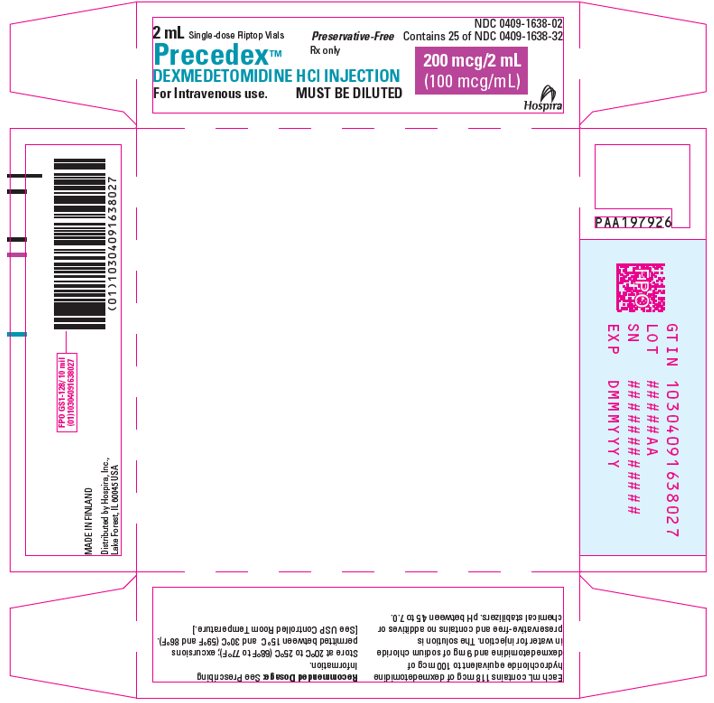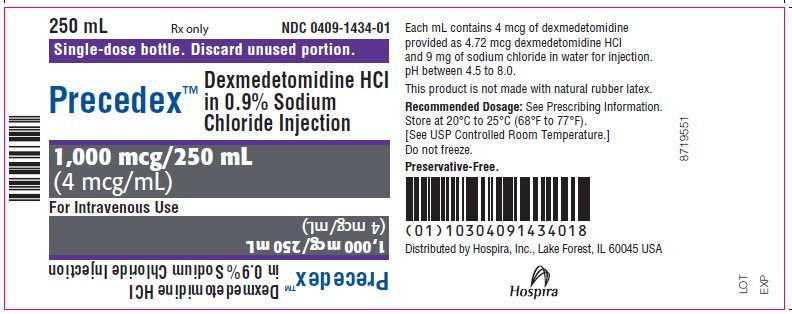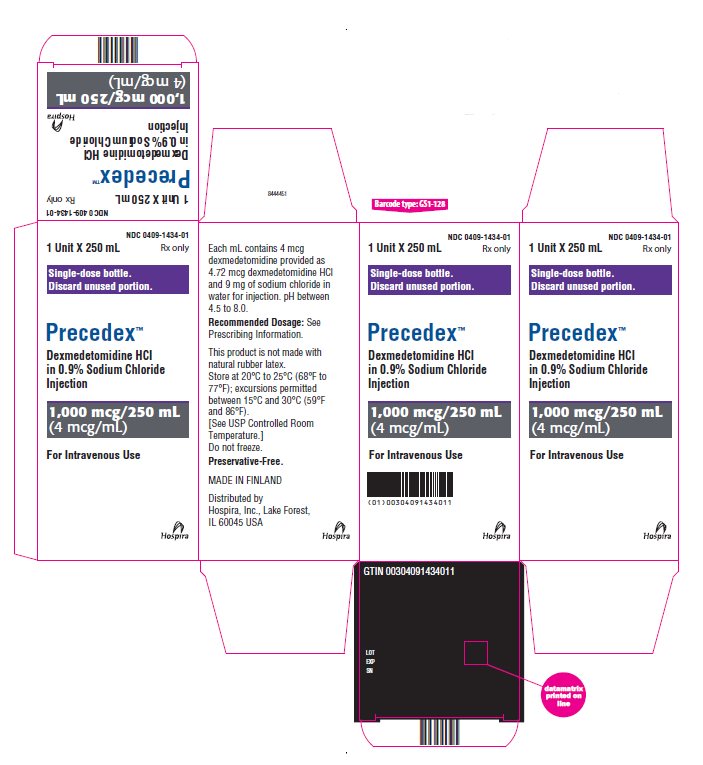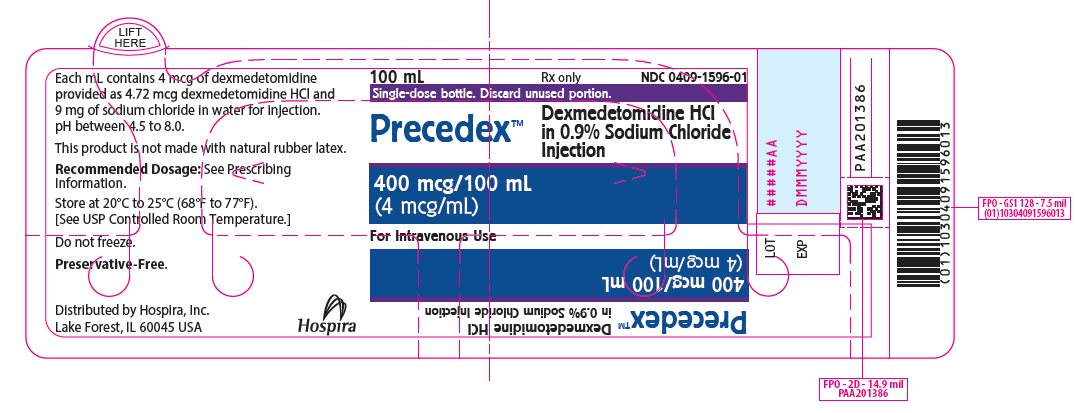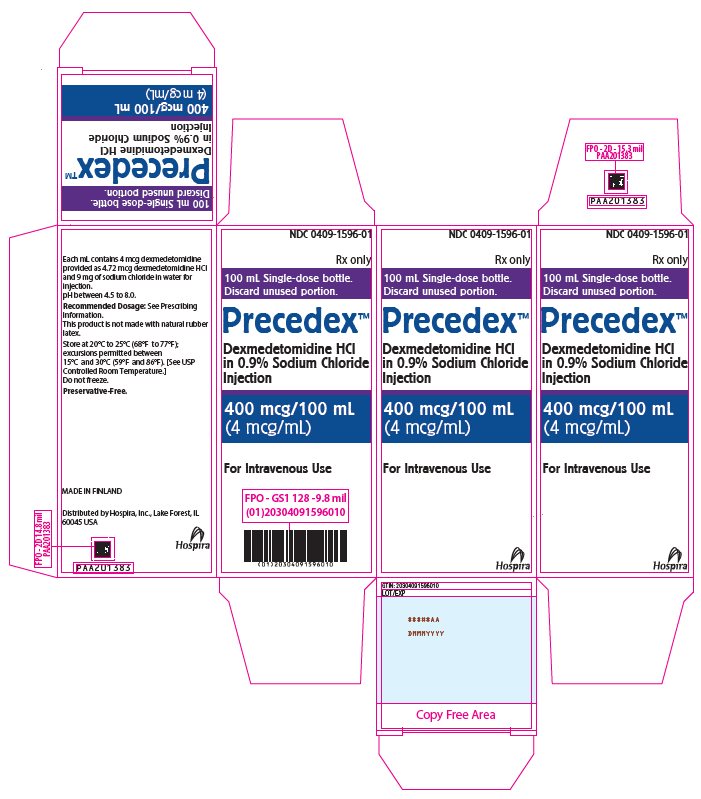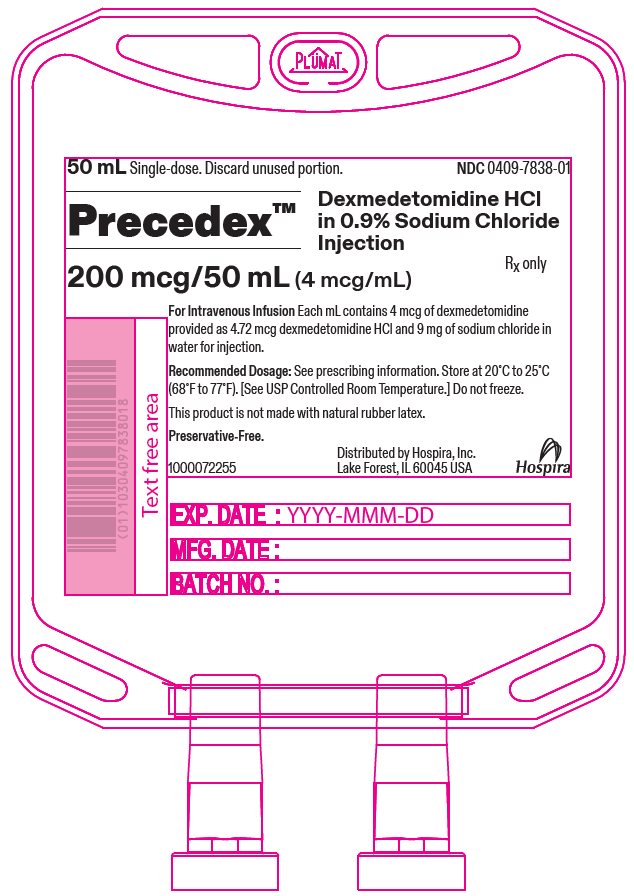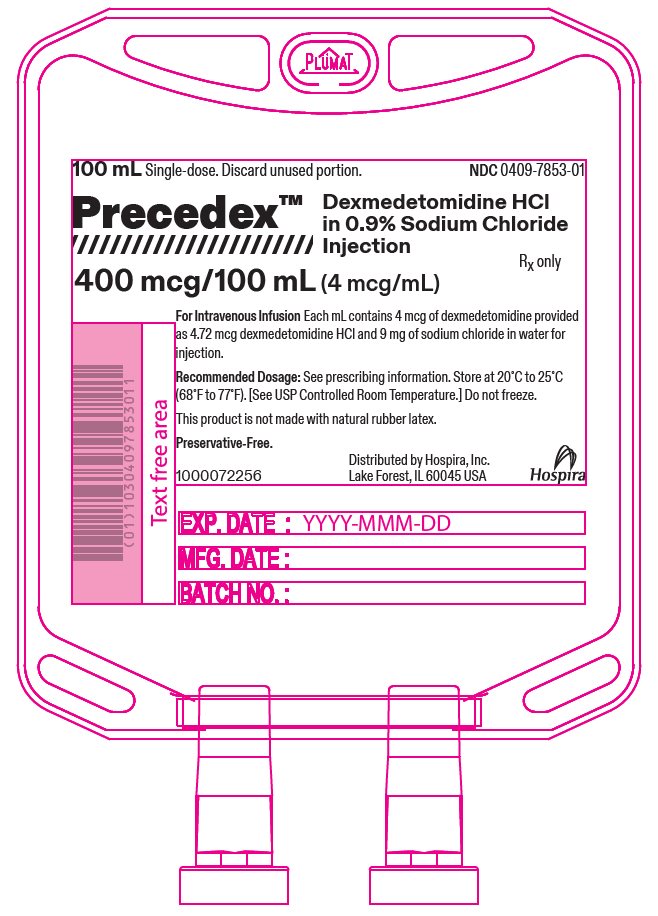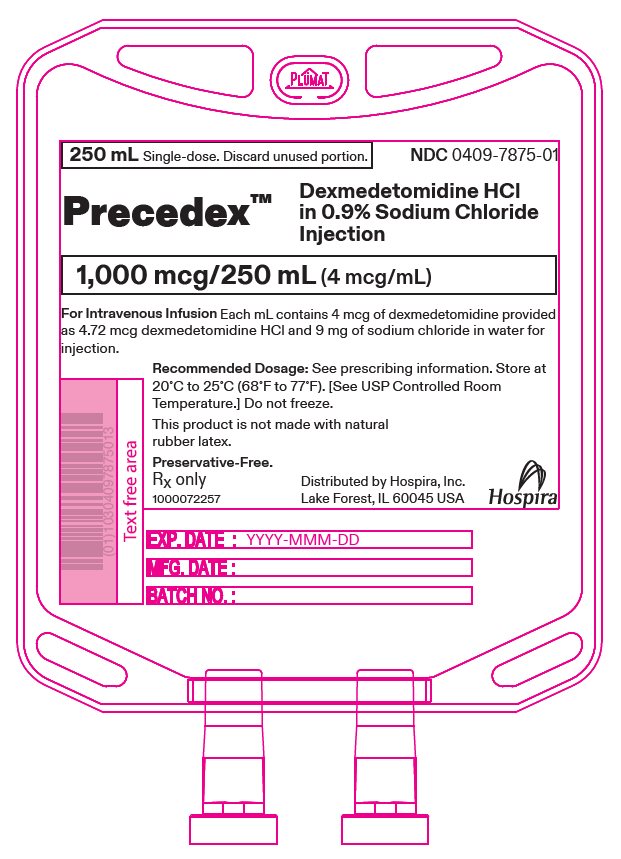 DRUG LABEL: Precedex
NDC: 0409-1660 | Form: INJECTION, SOLUTION
Manufacturer: Hospira, Inc.
Category: prescription | Type: HUMAN PRESCRIPTION DRUG LABEL
Date: 20260108

ACTIVE INGREDIENTS: DEXMEDETOMIDINE HYDROCHLORIDE 4 ug/1 mL
INACTIVE INGREDIENTS: SODIUM CHLORIDE 9 mg/1 mL; WATER

HIGHLIGHTS OF PRESCRIBING INFORMATION

These highlights do not include all the information needed to use PRECEDEX safely and effectively. See full prescribing information for PRECEDEX.
PRECEDEX™ (dexmedetomidine hydrochloride) injection, for intravenous use
PRECEDEX™ (dexmedetomidine hydrochloride) in sodium chloride injection, for intravenous use
Initial U.S. Approval: 1999

RECENT MAJOR CHANGES

Dosage and Administration, Preparation of Solution (2.4) | 10/2024

1 INDICATIONS AND USAGE

PRECEDEX is a alpha2-adrenergic receptor agonist indicated for:

- Sedation of initially intubated and mechanically ventilated adult patients during treatment in an intensive care setting. Administer PRECEDEX by continuous infusion not to exceed 24 hours. (1.1)
- Sedation of non-intubated adult patients prior to and/or during surgical and other procedures. (1.2)
- Sedation of non-intubated pediatric patients aged 1 month to less than 18 years prior to and during non-invasive procedures. (1.2)

2 DOSAGE AND ADMINISTRATION

- Individualize and titrate PRECEDEX dosing to desired clinical effect. (2.1)
- Administer PRECEDEX using a controlled infusion device. (2.1)
- Dilute the 200 mcg/2 mL (100 mcg/mL) vial contents in 0.9% sodium chloride solution to achieve required concentration (4 mcg/mL) prior to administration. (2.4)
- The 80 mcg/20 mL single-dose vial, and 200 mcg/50 mL, 400 mcg/100 mL, and 1,000 mcg/250 mL single-dose bottles and single-dose flexible containers do not require further dilution prior to administration. (2.4)
- For Adult Intensive Care Unit Sedation: Initiate at one mcg/kg over 10 minutes, followed by a maintenance infusion of 0.2 mcg/kg/hour to 0.7 mcg/kg/hour. (2.2)
- For Adult Procedural Sedation: Initiate at one mcg/kg over 10 minutes, followed by a maintenance infusion initiated at 0.6 mcg/kg/hour and titrated to achieve desired clinical effect with doses ranging from 0.2 mcg/kg/hour to 1 mcg/kg/hour. (2.2)
- For Sedation of Pediatric Patients During Non-invasive Procedures: Patients 1 month to less than 2 years old initiate at 1.5 mcg/kg over 10 minutes followed by a maintenance infusion of 1.5 mcg/kg/hour and titrated to achieve desired clinical effect with dosage ranging from 0.5 mcg/kg/hour to 1.5 mcg/kg/hour; patients 2 to less than 18 years old initiate at 2 mcg/kg over 10 minutes followed by a maintenance infusion of 1.5 mcg/kg/hour and titrated to achieve desired clinical effect with dosage ranging from 0.5 mcg/kg/hour to 1.5 mcg/kg/hour. (2.2)
- Alternative Doses: Recommended for patients over 65 years of age and awake fiberoptic intubation patients. (2.2)

3 DOSAGE FORMS AND STRENGTHS

- PRECEDEX Injection, 200 mcg/2 mL (100 mcg/mL) in a single-dose vial. To be used after dilution. (3)
- PRECEDEX in 0.9% Sodium Chloride Injection, 80 mcg/20 mL (4 mcg/mL) in a single-dose vial. Ready to use. (3)
- PRECEDEX in 0.9% Sodium Chloride Injection, 200 mcg/50 mL, 400 mcg/100 mL, and 1,000 mcg/250 mL (4 mcg/mL) in single-dose glass bottles. Ready to use. (3)
- PRECEDEX in 0.9% Sodium Chloride Injection, 200 mcg/50 mL, 400 mcg/100 mL, and 1,000 mcg/250 mL (4 mcg/mL) in single-dose flexible containers. Ready to use. (3)

4 CONTRAINDICATIONS

None. (4)

5 WARNINGS AND PRECAUTIONS

- Monitoring: Continuously monitor patients while receiving PRECEDEX. (5.1)
- Bradycardia and Sinus Arrest: Have occurred in young healthy volunteers with high vagal tone or with different routes of administration, e.g., rapid intravenous or bolus administration. (5.2)
- Hypotension and Bradycardia: May necessitate medical intervention. May be more pronounced in patients with hypovolemia, diabetes mellitus, or chronic hypertension, and in the elderly. Use with caution in patients with advanced heart block or severe ventricular dysfunction. (5.2)
- Co-administration with Other Vasodilators or Negative Chronotropic Agents: Use with caution due to additive pharmacodynamic effects. (5.2)
- Transient Hypertension: Observed primarily during the loading dose. Consider reduction in loading infusion rate. (5.3)
- Arousability: Patients can become aroused/alert with stimulation; this alone should not be considered as lack of efficacy. (5.4)
- Tolerance and Tachyphylaxis: Prolonged exposure to dexmedetomidine beyond 24 hours may be associated with tolerance and tachyphylaxis and a dose-related increase in adverse events. (5.6)

6 ADVERSE REACTIONS

- The most common adverse reactions (incidence >2%) in adults are hypotension, bradycardia, and dry mouth. (6.1)
- The most common adverse reactions (incidence >5%) in pediatric patients aged 1 month to less than 17 years are bradypnea, bradycardia, hypertension, and hypotension. (6.1)
- Adverse reactions in adults, associated with infusions >24 hours in duration include ARDS, respiratory failure, and agitation. (6.1)

To report SUSPECTED ADVERSE REACTIONS, contact Hospira, Inc. at 1-800-441-4100, or FDA at 1-800-FDA-1088 or www.fda.gov/medwatch.

7 DRUG INTERACTIONS

Anesthetics, Sedatives, Hypnotics, Opioids: Enhancement of pharmacodynamic effects. Reduction in dosage of PRECEDEX or the concomitant medication may be required. (7.1)

8 USE IN SPECIFIC POPULATIONS

- Geriatric Patients: Dose reduction should be considered. (2.2, 2.3, 5.2, 8.5)
- Hepatic Impairment: Dose reduction should be considered. (2.2, 2.3, 5.8, 8.6)

FULL PRESCRIBING INFORMATION

1 INDICATIONS AND USAGE

1.1 Intensive Care Unit Sedation

PRECEDEX is indicated for sedation of initially intubated and mechanically ventilated adult patients during treatment in an intensive care setting. PRECEDEX should be administered by continuous infusion not to exceed 24 hours.

PRECEDEX has been continuously infused in mechanically ventilated adult patients prior to extubation, during extubation, and post-extubation. It is not necessary to discontinue PRECEDEX prior to extubation.

1.2 Procedural Sedation

PRECEDEX is indicated for sedation of non-intubated adult patients prior to and/or during surgical and other procedures.

PRECEDEX is indicated for sedation of non-intubated pediatric patients aged 1 month to less than 18 years prior to and during non-invasive procedures.

2 DOSAGE AND ADMINISTRATION

2.1 Administration Instructions

- PRECEDEX dosing should be individualized and titrated to desired clinical response.
- PRECEDEX is not indicated for infusions lasting longer than 24 hours.
- PRECEDEX should be administered using a controlled infusion device.

2.2 Recommended Dosage

Table 1: Recommended Dosage in Adult Patients
INDICATION | DOSAGE AND ADMINISTRATION
Initiation of Intensive Care Unit Sedation | For adult patients: a loading infusion of one mcg/kg over 10 minutes.; For adult patients being converted from alternate sedative therapy: a loading dose may not be required.; For patients over 65 years of age: Consider a dose reduction [see Use in Specific Populations (8.5)].; For adult patients with impaired hepatic function: Consider a dose reduction [see Use in Specific Populations (8.6), Clinical Pharmacology (12.3)].
Maintenance of Intensive Care Unit Sedation | For adult patients: a maintenance infusion of 0.2 mcg/kg/hour to 0.7 mcg/kg/hour. The rate of the maintenance infusion should be adjusted to achieve the desired level of sedation.; For patients over 65 years of age: Consider a dose reduction [see Use in Specific Populations (8.5)].; For adult patients with impaired hepatic function: Consider a dose reduction [see Use in Specific Populations (8.6), Clinical Pharmacology (12.3)]
Initiation of Procedural Sedation | For adult patients: a loading infusion of one mcg/kg over 10 minutes. For less invasive procedures such as ophthalmic surgery, a loading infusion of 0.5 mcg/kg given over 10 minutes may be suitable.; For awake fiberoptic intubation in adult patients: a loading infusion of one mcg/kg over 10 minutes.; For patients over 65 years of age: a loading infusion of 0.5 mcg/kg over 10 minutes [see Use in Specific Populations (8.5)].; For adult patients with impaired hepatic function: Consider a dose reduction [see Use in Specific Populations (8.6), Clinical Pharmacology (12.3)].
Maintenance of Procedural Sedation | For adult patients: the maintenance infusion is generally initiated at 0.6 mcg/kg/hour and titrated to achieve desired clinical effect with doses ranging from 0.2 mcg/kg/hour to 1 mcg/kg/hour. Adjust the rate of the maintenance infusion to achieve the targeted level of sedation.; For awake fiberoptic intubation in adult patients: a maintenance infusion of 0.7 mcg/kg/hour is recommended until the endotracheal tube is secured.; For patients over 65 years of age: Consider a dose reduction [see Use in Specific Populations (8.5)].; For adult patients with impaired hepatic function: Consider a dose reduction [see Use in Specific Populations (8.6), Clinical Pharmacology (12.3)].

Table 2: Recommended Dosage in Pediatric Patients
INDICATION | DOSAGE AND ADMINISTRATION
Initiation of Sedation During Non‑invasive Procedures | For pediatric patients:; - 1 month to less than 2 years: a loading infusion of 1.5 mcg/kg over 10 minutes. - 2 to less than 18 years: a loading infusion of 2 mcg/kg over 10 minutes.; Consider a reduction in dosage if clinically indicated.
Maintenance of Sedation During Non-invasive Procedures | For pediatric patients:; - 1 month to less than 18 years: the maintenance infusion is generally initiated at 1.5 mcg/kg/hour and titrated to achieve desired clinical effect with dosage ranging from 0.5 mcg/kg/hour to 1.5 mcg/kg/hour.; As clinically warranted, titrate the maintenance dose to individual patient clinical response.

2.3 Dosage Adjustment

Due to possible pharmacodynamic interactions, a reduction in dosage of PRECEDEX or other concomitant anesthetics, sedatives, hypnotics or opioids may be required when co-administered [see Drug Interactions (7.1)].

Dosage reductions may need to be considered for adult patients with hepatic impairment, and geriatric patients [see Warnings and Precautions (5.8), Use in Specific Populations (8.6), Clinical Pharmacology (12.3)].

2.4 Preparation of Solution

Strict aseptic technique must always be maintained during handling of PRECEDEX.

Parenteral drug products should be inspected visually for particulate matter and discoloration prior to administration, whenever solution and container permit. Do not use if product is discolored or if precipitate matter is present.

PRECEDEX Presentations Requiring Dilution:

- PRECEDEX Injection, 200 mcg/2 mL (100 mcg/mL)

PRECEDEX must be diluted with 0.9% sodium chloride injection to achieve required concentration (4 mcg/mL) prior to administration. Preparation of solutions is the same, whether for the loading dose or maintenance infusion.

To prepare the infusion, withdraw 2 mL of PRECEDEX Injection, and add to 48 mL of 0.9% sodium chloride injection to a total of 50 mL. Shake gently to mix well.

PRECEDEX Presentations that are Ready to Use:

PRECEDEX in 0.9% Sodium Chloride Injection is supplied in glass containers and flexible containers:

- 80 mcg/20 mL (4 mcg/mL) in glass vials
- 200 mcg/50 mL (4 mcg/mL) in glass bottles and flexible containers
- 400 mcg/100 mL (4 mcg/mL) in glass bottles and flexible containers
- 1,000 mcg/250 mL (4 mcg/mL) in glass bottles and flexible containers

These presentations contain a premixed, ready to use dexmedetomidine hydrochloride solution in 0.9% sodium chloride in water. No further dilution of these preparations is necessary.

Instructions for Use for Flexible Containers:

1. Tear outer wrap at the notch and remove solution container.
2. Check the container for minute leaks by squeezing it firmly. If leaks are found, or if the seal is not intact, discard the solution as the sterility may be compromised.
3. Do not use if the solution is cloudy or a precipitate is present.
4. Use aseptic technique.

Preparation for Administration:

1. Close flow control clamp of administration set.
2. Remove twist-off cap from administration port at bottom of flexible container.
3. Insert spike of administration set into administration port with a twisting motion until the spike is firmly seated. NOTE: See full directions on administration set carton.
4. Suspend container from hanger.
5. Squeeze and release drip chamber to establish proper fluid level in chamber during infusion.
6. Open flow control clamp to expel air from set. Close clamp.
7. Regulate rate of administration with flow control clamp.

2.5 Administration with Other Fluids

PRECEDEX infusion should not be co-administered through the same intravenous catheter with blood or plasma because physical compatibility has not been established.

PRECEDEX has been shown to be incompatible when administered with the following drugs: amphotericin B, diazepam.

PRECEDEX has been shown to be compatible when administered with the following intravenous fluids:

- 0.9% sodium chloride in water
- 5% dextrose in water
- 20% mannitol
- Lactated Ringer's solution
- 100 mg/mL magnesium sulfate solution
- 0.3% potassium chloride solution

2.6 Compatibility with Natural Rubber

Compatibility studies have demonstrated the potential for absorption of PRECEDEX to some types of natural rubber. Although PRECEDEX is dosed to effect, it is advisable to use administration components made with synthetic or coated natural rubber gaskets.

3 DOSAGE FORMS AND STRENGTHS

PRECEDEX Presentations Requiring Dilution:

PRECEDEX (dexmedetomidine hydrochloride) injection is a clear and colorless solution, to be used after dilution. It is available as:

- 200 mcg/2 mL (100 mcg/mL) single-dose vial.

PRECEDEX Presentations that are Ready To Use:

PRECEDEX (dexmedetomidine hydrochloride) in 0.9% sodium chloride injection is a clear and colorless solution, ready to use. It is available as:

- PRECEDEX 80 mcg/20 mL (4 mcg/mL) single-dose vial.
- PRECEDEX 200 mcg/50 mL (4 mcg/mL) single-dose glass bottle.
- PRECEDEX 400 mcg/100 mL (4 mcg/mL) single-dose glass bottle.
- PRECEDEX 1,000 mcg/250 mL (4 mcg/mL) single-dose glass bottle.
- PRECEDEX 200 mcg/50 mL (4 mcg/mL) single-dose flexible container.
- PRECEDEX 400 mcg/100 mL (4 mcg/mL) single-dose flexible container.
- PRECEDEX 1,000 mcg/250 mL (4 mcg/mL) single-dose flexible container.

4 CONTRAINDICATIONS

None.

5 WARNINGS AND PRECAUTIONS

5.1 Drug Administration

PRECEDEX should be administered only by persons skilled in the management of patients in the intensive care or operating room setting. Due to the known pharmacological effects of PRECEDEX, patients should be continuously monitored while receiving PRECEDEX.

5.2 Hypotension, Bradycardia, and Sinus Arrest

Clinically significant episodes of bradycardia and sinus arrest have been reported with PRECEDEX administration in young, healthy adult volunteers with high vagal tone or with different routes of administration including rapid intravenous or bolus administration.

Reports of hypotension and bradycardia have been associated with PRECEDEX infusion. Some of these cases have resulted in fatalities. If medical intervention is required, treatment may include decreasing or stopping the infusion of PRECEDEX, increasing the rate of intravenous fluid administration, elevation of the lower extremities, and use of pressor agents. Because PRECEDEX has the potential to augment bradycardia induced by vagal stimuli, clinicians should be prepared to intervene. The intravenous administration of anticholinergic agents (e.g., glycopyrrolate, atropine) should be considered to modify vagal tone. In clinical trials, glycopyrrolate or atropine were effective in the treatment of most episodes of PRECEDEX-induced bradycardia. However, in some patients with significant cardiovascular dysfunction, more advanced resuscitative measures were required.

Caution should be exercised when administering PRECEDEX to patients with advanced heart block and/or severe ventricular dysfunction. Because PRECEDEX decreases sympathetic nervous system activity, hypotension and/or bradycardia may be expected to be more pronounced in patients with hypovolemia, diabetes mellitus, or chronic hypertension and in elderly patients.

In clinical trials where other vasodilators or negative chronotropic agents were co-administered with PRECEDEX an additive pharmacodynamic effect was not observed. Nonetheless, caution should be used when such agents are administered concomitantly with PRECEDEX.

5.3 Transient Hypertension

Transient hypertension has been observed primarily during the loading dose in association with the initial peripheral vasoconstrictive effects of PRECEDEX. Treatment of the transient hypertension has generally not been necessary, although reduction of the loading infusion rate may be desirable.

5.4 Arousability

Some patients receiving PRECEDEX have been observed to be arousable and alert when stimulated. This alone should not be considered as evidence of lack of efficacy in the absence of other clinical signs and symptoms.

5.5 Withdrawal

Intensive Care Unit Sedation

With administration up to 7 days, regardless of dose, 12 (5%) PRECEDEX adult subjects experienced at least 1 event related to withdrawal within the first 24 hours after discontinuing study drug and 7 (3%) PRECEDEX adult subjects experienced at least 1 event 24 to 48 hours after end of study drug. The most common events were nausea, vomiting, and agitation [see Adverse Reactions (6.1)].

In adult subjects, tachycardia and hypertension requiring intervention in the 48 hours following study drug discontinuation occurred at frequencies of <5%.

Procedural Sedation

In adult subjects, withdrawal symptoms were not seen after discontinuation of short‑term infusions of PRECEDEX (<6 hours).

In pediatric patients, mild transient withdrawal symptoms of emergence delirium or agitation were seen after discontinuation of short‑term infusions of PRECEDEX (<2 hours) [see Adverse Reactions (6.1)].

5.6 Tolerance and Tachyphylaxis

Use of dexmedetomidine beyond 24 hours has been associated with tolerance and tachyphylaxis and a dose‑related increase in adverse reactions [see Adverse Reactions (6.1)].

5.7 Hyperthermia or Pyrexia

PRECEDEX may induce hyperthermia or pyrexia, which may be resistant to traditional cooling methods, such as administration of cooled intravenous fluids and antipyretic medications. Discontinue PRECEDEX if drug‑related hyperthermia or pyrexia is suspected and monitor patients until body temperature normalizes.

5.8 Hepatic Impairment

Since PRECEDEX clearance decreases with severity of hepatic impairment, dose reduction should be considered in patients with impaired hepatic function [see Dosage and Administration (2.2, 2.3)].

6 ADVERSE REACTIONS

The following clinically significant adverse reactions are described elsewhere in the labeling:

- Hypotension, bradycardia and sinus arrest [see Warnings and Precautions (5.2)]
- Transient hypertension [see Warnings and Precautions (5.3)]

6.1 Clinical Trials Experience

Because clinical trials are conducted under widely varying conditions, adverse reactions rates observed in the clinical trials of a drug cannot be directly compared to rates in the clinical trials of another drug and may not reflect the rates observed in practice.

Most common treatment-emergent adverse reactions, occurring in greater than 2% of adult patients in both Intensive Care Unit and procedural sedation studies include hypotension, bradycardia and dry mouth.

Intensive Care Unit Sedation

Adverse reaction information is derived from the continuous infusion trials of PRECEDEX for sedation in the Intensive Care Unit setting in which 1,007 adult patients received PRECEDEX. The mean total dose was 7.4 mcg/kg (range: 0.8 to 84.1), mean dose per hour was 0.5 mcg/kg/hr (range: 0.1 to 6.0) and the mean duration of infusion of 15.9 hours (range: 0.2 to 157.2). The population was between 17 to 88 years of age, 43% ≥65 years of age, 77% male and 93% Caucasian. Treatment-emergent adverse reactions occurring at an incidence of >2% are provided in Table 3. The most frequent adverse reactions were hypotension, bradycardia and dry mouth [see Warnings and Precautions (5.2)].

Table 3: Adverse Reactions with an Incidence >2%-Adult Intensive Care Unit Sedation Population <24 hours [26 subjects in the all PRECEDEX group and 10 subjects in the randomized PRECEDEX group had exposure for greater than 24 hours.]
Adverse Event | All PRECEDEX (N = 1007) (%) | Randomized PRECEDEX (N = 798) (%) | Placebo (N = 400) (%) | Propofol (N = 188) (%)
Hypotension | 25% | 24% | 12% | 13%
Hypertension | 12% | 13% | 19% | 4%
Nausea | 9% | 9% | 9% | 11%
Bradycardia | 5% | 5% | 3% | 0
Atrial Fibrillation | 4% | 5% | 3% | 7%
Pyrexia | 4% | 4% | 4% | 4%
Dry Mouth | 4% | 3% | 1% | 1%
Vomiting | 3% | 3% | 5% | 3%
Hypovolemia | 3% | 3% | 2% | 5%
Atelectasis | 3% | 3% | 3% | 6%
Pleural Effusion | 2% | 2% | 1% | 6%
Agitation | 2% | 2% | 3% | 1%
Tachycardia | 2% | 2% | 4% | 1%
Anemia | 2% | 2% | 2% | 2%
Hyperthermia | 2% | 2% | 3% | 0
Chills | 2% | 2% | 3% | 2%
Hyperglycemia | 2% | 2% | 2% | 3%
Hypoxia | 2% | 2% | 2% | 3%
Post-procedural Hemorrhage | 2% | 2% | 3% | 4%
Pulmonary Edema | 1% | 1% | 1% | 3%
Hypocalcemia | 1% | 1% | 0 | 2%
Acidosis | 1% | 1% | 1% | 2%
Urine Output Decreased | 1% | 1% | 0 | 2%
Sinus Tachycardia | 1% | 1% | 1% | 2%
Ventricular Tachycardia | <1% | 1% | 1% | 5%
Wheezing | <1% | 1% | 0 | 2%
Edema Peripheral | <1% | 0 | 1% | 2%

Adverse reaction information was also derived from the placebo-controlled, continuous infusion trials of PRECEDEX for sedation in the surgical intensive care unit setting in which 387 adult patients received PRECEDEX for less than 24 hours. The most frequently observed treatment-emergent adverse events included hypotension, hypertension, nausea, bradycardia, fever, vomiting, hypoxia, tachycardia and anemia (see Table 4).

Table 4: Treatment-Emergent Adverse Events Occurring in >1% of All Dexmedetomidine-Treated Adult Patients in the Randomized Placebo-Controlled Continuous Infusion <24 Hours ICU Sedation Studies
Adverse Event | Randomized Dexmedetomidine (N = 387) | Placebo (N = 379)
Hypotension | 28% | 13%
Hypertension | 16% | 18%
Nausea | 11% | 9%
Bradycardia | 7% | 3%
Fever | 5% | 4%
Vomiting | 4% | 6%
Atrial Fibrillation | 4% | 3%
Hypoxia | 4% | 4%
Tachycardia | 3% | 5%
Hemorrhage | 3% | 4%
Anemia | 3% | 2%
Dry Mouth | 3% | 1%
Rigors | 2% | 3%
Agitation | 2% | 3%
Hyperpyrexia | 2% | 3%
Pain | 2% | 2%
Hyperglycemia | 2% | 2%
Acidosis | 2% | 2%
Pleural Effusion | 2% | 1%
Oliguria | 2% | <1%
Thirst | 2% | <1%

In a controlled clinical trial, PRECEDEX was compared to midazolam for ICU sedation exceeding 24 hours duration in adult patients. Key treatment emergent adverse events occurring in dexmedetomidine or midazolam treated adult patients in the randomized active comparator continuous infusion long-term intensive care unit sedation study are provided in Table 5. The number (%) of adult subjects who had a dose-related increase in treatment‑emergent adverse events by maintenance adjusted dose rate range in the PRECEDEX group is provided in Table 6.

Table 5: Key Treatment-Emergent Adverse Events Occurring in Dexmedetomidine- or Midazolam‑Treated Adult Patients in the Randomized Active Comparator Continuous Infusion Long‑Term Intensive Care Unit Sedation Study
Adverse Event | Dexmedetomidine (N = 244) | Midazolam (N = 122)
Hypotension [Hypotension was defined in absolute terms as Systolic blood pressure of <80 mmHg or Diastolic blood pressure of <50 mmHg or in relative terms as ≤30% lower than pre-study drug infusion value.] | 56% | 56%
Hypotension Requiring Intervention | 28% | 27%
Bradycardia [Bradycardia was defined in absolute terms as <40 bpm or in relative terms as ≤30% lower than pre-study drug infusion value.] | 42% | 19%
Bradycardia Requiring Intervention | 5% | 1%
Systolic Hypertension [Hypertension was defined in absolute terms as Systolic blood pressure >180 mmHg or Diastolic blood pressure of >100 mmHg or in relative terms as ≥30% higher than pre-study drug infusion value.] | 28% | 42%
Tachycardia [Tachycardia was defined in absolute terms as >120 bpm or in relative terms as ≥30% greater than pre-study drug infusion value.] | 25% | 44%
Tachycardia Requiring Intervention | 10% | 10%
Diastolic Hypertension | 12% | 15%
Hypertension | 11% | 15%
Hypertension Requiring Intervention [Includes any type of hypertension] | 19% | 30%
Hypokalemia | 9% | 13%
Pyrexia | 7% | 2%
Agitation | 7% | 6%
Hyperglycemia | 7% | 2%
Constipation | 6% | 6%
Hypoglycemia | 5% | 6%
Respiratory Failure | 5% | 3%
Renal Failure Acute | 2% | 1%
Acute Respiratory Distress Syndrome | 2% | 1%
Generalized Edema | 2% | 6%
Hypomagnesemia | 1% | 7%

The following adverse events occurred between 2 and 5% for PRECEDEX and Midazolam, respectively: renal failure acute (2.5%, 0.8%), acute respiratory distress syndrome (2.5%, 0.8%), and respiratory failure (4.5%, 3.3%).

Table 6: Number (%) of Adult Subjects Who Had a Dose-Related Increase in Treatment Emergent Adverse Events by Maintenance Adjusted Dose Rate Range in the PRECEDEX Group
PRECEDEX (mcg/kg/hr)
Adverse Event | ≤0.7 [Average maintenance dose over the entire study drug administration.] (N = 95) | >0.7 to ≤1.1 (N = 78) | >1.1 (N = 71)
Constipation | 6% | 5% | 14%
Agitation | 5% | 8% | 14%
Anxiety | 5% | 5% | 9%
Edema Peripheral | 3% | 5% | 7%
Atrial Fibrillation | 2% | 4% | 9%
Respiratory Failure | 2% | 6% | 10%
Acute Respiratory Distress Syndrome | 1% | 3% | 9%

Adult Procedural Sedation

Adverse reaction information is derived from the two trials for adult procedural sedation [see Clinical Studies (14.2)] in which 318 adult patients received PRECEDEX. The mean total dose was 1.6 mcg/kg (range: 0.5 to 6.7), mean dose per hour was 1.3 mcg/kg/hr (range: 0.3 to 6.1) and the mean duration of infusion of 1.5 hours (range: 0.1 to 6.2). The population was between 18 to 93 years of age, ASA I–IV, 30% ≥65 years of age, 52% male and 61% Caucasian.

Treatment-emergent adverse reactions occurring in adults at an incidence of >2% are provided in Table 7. The most frequent adverse reactions were hypotension, bradycardia, and dry mouth [see Warnings and Precautions (5.2)]. Pre-specified criteria for the vital signs to be reported as adverse reactions are footnoted below the table. The decrease in respiratory rate and hypoxia was similar between PRECEDEX and comparator groups in both studies.

Table 7: Adverse Reactions with an Incidence >2%—Adult Procedural Sedation Population
Adverse Event | PRECEDEX (N = 318) (%) | Placebo (N = 113) (%)
Hypotension [Hypotension was defined in absolute and relative terms as Systolic blood pressure of <80 mmHg or ≤30% lower than pre-study drug infusion value, or Diastolic blood pressure of <50 mmHg.] | 54% | 30%
Respiratory Depression [Respiratory depression was defined in absolute and relative terms as respiratory rate (RR) <8 beats per minute or >25% decrease from baseline.] | 37% | 32%
Bradycardia [Bradycardia was defined in absolute and relative terms as <40 beats per minute or ≤30% lower than pre-study drug infusion value. Subjects in Study 2 were pretreated with glycopyrrolate 0.1 mg intravenously before receiving study drug [see Clinical Studies (14.2)].] | 14% | 4%
Hypertension [Hypertension was defined in absolute and relative terms as Systolic blood pressure >180 mmHg or ≥30% higher than pre-study drug infusion value or Diastolic blood pressure of >100 mmHg.] | 13% | 24%
Tachycardia [Tachycardia was defined in absolute and relative terms as >120 beats per minute or ≥30% greater than pre-study drug infusion value.] | 5% | 17%
Nausea | 3% | 2%
Dry Mouth | 3% | 1%
Hypoxia [Hypoxia was defined in absolute and relative terms as SpO2 <90% or 10% decrease from baseline.] | 2% | 3%
Bradypnea | 2% | 4%

Pediatric Sedation for Magnetic Resonance Imaging

Adverse reaction information is derived from a trial for sedation of pediatric procedural during a non‑invasive procedure [see Clinical Studies (14.2)] in which 122 pediatric patients aged 1 month to less than 17 years undergoing magnetic resonance imaging (MRI) scans received PRECEDEX. In pediatric patients 1 month to less than 2 years old, the median total dose for the PRECEDEX low, middle, and high dose treatment groups was 8.30, 18.90, and 22.75 mcg, respectively. The median duration of treatment ranged from 52.5 to 69 minutes across treatment groups. In pediatric patients 2 to less than 17 years old, the median total dose for the PRECEDEX low, middle, and high dose treatment groups was 21.30, 43.90, and 80.25 mcg, respectively. The median duration of treatment ranged from 56.5 to 66 minutes across treatment groups.

All-causality treatment-emergent adverse reactions occurring in the combined age group of pediatric patients during the procedure at an incidence of >5% are provided in Table 8. The most frequent treatment-emergent adverse events were bradypnea, bradycardia, hypertension, and hypotension [see Warnings and Precautions (5.2, 5.3)]. In the combined age group and in each age group, increased incidence in bradycardia and hypertension was observed with increasing PRECEDEX dose. Mild transient withdrawal symptoms of emergence delirium or agitation occurred in 3 of 122 patients after discontinuation of PRECEDEX infusion [see Warnings and Precautions (5.5)]. All reported treatment‑emergent adverse reactions were mild to moderate in severity and the majority resolved without medical intervention. No subject in the study required airway intervention, including a jaw thrust or insertion of a nasal or oral airway. A similar profile was observed in the pediatric patients 1 month to less than 2 years old and in pediatric patients 2 to less than 17 years old. Pre‑specified criteria for the vital signs to be reported as adverse events are footnoted below the table.

Table 8: Treatment-Emergent Adverse Events with Incidence >5%—Pediatric Patients During Non-invasive Procedure
 | PRECEDEX; Low Dose; (N = 42) | PRECEDEX; Middle Dose; (N = 42) | PRECEDEX; High Dose; (N = 38) | Total; (N = 122)
Number (%) of Pediatric Patients | n (%) | n (%) | n (%) | n (%)
Adverse Event
Bradypnea [Bradypnea was defined as respiratory rate <1st centile of the age adjusted normal range.] | 33 (79) | 27 (64) | 22 (58) | 82 (67)
Bradycardia [Bradycardia was defined as a decrease in HR of 30% from baseline or absolute HR ≤1st centile of the age adjusted normal range.] | 24 (57) | 24 (57) | 27 (71) | 75 (62)
Hypertension [For pediatric patients 1 month to less than 1 year old, hypertension was defined as supine systolic blood pressure ≥104 mm/Hg and/or diastolic blood pressure ≥56 mmHg measurements. For pediatric patients 1 to less than 17 years old: hypertension was defined as supine systolic blood pressure and/or diastolic blood pressure measurements ≥95th percentile for gender, age, and height.] | 11 (26) | 17 (41) | 18 (47) | 46 (38)
Hypotension [Hypotension was defined as a decrease in systolic blood pressure ≥30% from baseline.] | 13 (31) | 11 (26) | 6 (16) | 30 (25)
Hypoxia [Hypoxia was defined as oxygen saturation <90% for any duration.] | 6 (14) | 3 (7) | 1 (3) | 10 (8)
Diastolic Hypertension | 3 (7) | 3 (7) | 4 (11) | 10 (8)
Systolic Hypertension | 1 (2) | 5 (12) | 3 (8) | 9 (7)
Tachycardia | 3 (7) | 1 (2) | 1 (3) | 5 (4)
N = Number of pediatric patients evaluable for adverse events.

6.2 Postmarketing Experience

The following adverse reactions have been identified during post‑approval use of PRECEDEX. Because these reactions are reported voluntarily from a population of uncertain size, it is not always possible to reliably estimate their frequency or establish a causal relationship to drug exposure.

Hypotension and bradycardia were the most common adverse reactions associated with the use of PRECEDEX during post‑approval use of the drug.

Table 9: Adverse Reactions Experienced During Post-Approval Use of PRECEDEX
System Organ Class | Preferred Term
Blood and Lymphatic System Disorders | Anemia
Cardiac Disorders | Arrhythmia, atrial fibrillation, atrioventricular block, bradycardia, cardiac arrest, cardiac disorder, extrasystoles, myocardial infarction, supraventricular tachycardia, tachycardia, ventricular arrhythmia, ventricular tachycardia
Eye Disorders | Photopsia, visual impairment
Gastrointestinal Disorders | Abdominal pain, diarrhea, nausea, vomiting
General Disorders and Administration Site Conditions | Chills, hyperpyrexia, pain, pyrexia, thirst
Hepatobiliary Disorders | Hepatic function abnormal, hyperbilirubinemia
Investigations | Alanine aminotransferase increased, aspartate aminotransferase increased, blood alkaline phosphatase increased, blood urea increased, electrocardiogram T wave inversion, gammaglutamyltransferase increased, electrocardiogram QT prolonged
Metabolism and Nutrition Disorders | Acidosis, hyperkalemia, hypoglycemia, hypovolemia, hypernatremia
Nervous System Disorders | Convulsion, dizziness, headache, neuralgia, neuritis, speech disorder
Psychiatric Disorders | Agitation, confusional state, delirium, hallucination, illusion
Renal and Urinary Disorders | Oliguria, polyuria
Respiratory, Thoracic and Mediastinal Disorders | Apnea, bronchospasm, dyspnea, hypercapnia, hypoventilation, hypoxia, pulmonary congestion, respiratory acidosis
Skin and Subcutaneous Tissue Disorders | Hyperhidrosis, pruritus, rash, urticaria
Surgical and Medical Procedures | Light anesthesia
Vascular Disorders | Blood pressure fluctuation, hemorrhage, hypertension, hypotension

7 DRUG INTERACTIONS

7.1 Anesthetics, Sedatives, Hypnotics, Opioids

Co-administration of PRECEDEX with anesthetics, sedatives, hypnotics, and opioids is likely to lead to an enhancement of effects. Specific studies have confirmed these effects with sevoflurane, isoflurane, propofol, alfentanil, and midazolam. No pharmacokinetic interactions between PRECEDEX and isoflurane, propofol, alfentanil and midazolam have been demonstrated. However, due to possible pharmacodynamic interactions, when co-administered with PRECEDEX, a reduction in dosage of PRECEDEX or the concomitant anesthetic, sedative, hypnotic or opioid may be required.

7.2 Neuromuscular Blockers

In one study of 10 healthy adult volunteers, administration of PRECEDEX for 45 minutes at a plasma concentration of one ng/mL resulted in no clinically meaningful increases in the magnitude of neuromuscular blockade associated with rocuronium administration.

8 USE IN SPECIFIC POPULATIONS

8.1 Pregnancy

Risk Summary

Available data from published randomized controlled trials and case reports over several decades of use with intravenously administered dexmedetomidine during pregnancy have not identified a drug-associated risk of major birth defects and miscarriage; however, the reported exposures occurred after the first trimester. Most of the available data are based on studies with exposures that occurred at the time of caesarean section delivery, and these studies have not identified an adverse effect on maternal outcomes or infant Apgar scores. Available data indicate that dexmedetomidine crosses the placenta.

In animal reproduction studies, fetal toxicity that lower fetal viability and reduced live fetuses occurred with subcutaneous administration of dexmedetomidine to pregnant rats during organogenesis at doses 1.8 times the maximum recommended human dose (MRHD) of 17.8 mcg/kg/day.

Developmental toxicity (low pup weights and adult offspring weights, decreased F1 grip strength, increased early implantation loss and decreased viability of second-generation offspring) occurred when pregnant rats were subcutaneously administered dexmedetomidine at doses less than the clinical dose from late pregnancy through lactation and weaning (see Data).

The estimated background risk of major birth defects and miscarriage for the indicated population is unknown. All pregnancies have a background risk of birth defect, loss, or other adverse outcomes. In the U.S. general population, the estimated background risk of major birth defects and miscarriage in clinically recognized pregnancies is 2–4% and 15–20%, respectively.

Data

Animal Data

Increased post-implantation losses and reduced live fetuses in the presence of maternal toxicity (i.e. decreased body weight) were noted in a rat embryo-fetal development study in which pregnant dams were administered subcutaneous doses of dexmedetomidine 200 mcg/kg/day (equivalent to 1.8 times the intravenous MRHD of 17.8 mcg/kg/day based on body surface area [BSA]) during the period of organogenesis (Gestation Day [GD] 6 to 15). No malformations were reported.

No malformations or embryo-fetal toxicity were noted in a rabbit embryo-fetal development study in which pregnant does were administered dexmedetomidine intravenously at doses of up to 96 mcg/kg/day (approximately half the human exposure at the MRHD based on AUC) during the period of organogenesis (GD 6 to 18).

Reduced pup and adult offspring birth weights, and grip strength were reported in a rat developmental toxicology study in which pregnant females were administered dexmedetomidine subcutaneously at doses of 8 mcg/kg/day (0.07 times the MRHD based on BSA) during late pregnancy through lactation and weaning (GD 16 to postnatal day [PND] 25). Decreased viability of second generation offspring and an increase in early implantation loss along with delayed motor development occurred in the 32 mcg/kg/day group (equivalent to less than the clinical dose based on BSA) when first generation offspring were allowed to mate. This study limited dosing to hard palate closure (GD 15 to 18) through weaning instead of dosing from implantation (GD 6 to 7) to weaning (PND 21).

In a study in the pregnant rat, placental transfer of dexmedetomidine was observed when radiolabeled dexmedetomidine was administered subcutaneously.

8.2 Lactation

Risk Summary

Available published literature reports the presence of dexmedetomidine in human milk following intravenous administration (see Data). There is no information regarding the effects of dexmedetomidine on the breastfed infant or the effects on milk production. Advise women to monitor the breastfed infant for irritability. The developmental and health benefits of breastfeeding should be considered along with the mother's clinical need for PRECEDEX and any potential adverse effects on the breastfed infant from PRECEDEX or from the underlying condition.

Data

In two published clinical studies, a total of 14 women were given intravenous dexmedetomidine 6 mcg/kg/hour for 10 minutes after delivery followed by continuous infusion of 0.2 mcg/kg/hour to 0.7 mcg/kg/hour. Breast milk and maternal blood samples were collected at 0, 6, 12, and 24 hours after discontinuation of dexmedetomidine. Plasma and milk dexmedetomidine concentrations were detectable up to 6 hours in most subjects, up to 12 hours in one subject and undetectable in all at 24 hours. The milk-to-plasma ratio from single paired maternal milk and plasma concentrations at each time point ranged from 0.53 to 0.95. The relative infant dose was estimated to range from 0.02 to 0.098%.

8.4 Pediatric Use

Sedation for Non-Invasive Procedures

The safety and efficacy of PRECEDEX have been established in pediatric patients 1 month to less than 18 years of age for sedation during non-invasive procedures. Use in this age group is based on one randomized double-blind, dose-ranging safety and efficacy trial in non-intubated pediatric patients 1 month to less than 17 years of age who required sedation prior to undergoing MRI scans [see Clinical Studies (14.2)]. An increase in frequency of bradypnea, bradycardia, hypertension and hypotension was observed in pediatric patients treated with PRECEDEX [see Adverse Reactions (6.1)]. The overall safety profile of PRECEDEX in pediatric patients was consistent with the known safety profile in adults [see Adverse Reactions (6.1)].

The safety and effectiveness of PRECEDEX have not been established in pediatric patients less than 1 month of age.

ICU Sedation

The safety and efficacy of PRECEDEX have not been established in pediatric patients for ICU sedation. One assessor-blinded trial in pediatric patients and two open label studies in neonates were conducted to assess efficacy for ICU sedation. These studies did not meet their primary efficacy endpoints and the safety data submitted were insufficient to fully characterize the safety profile of PRECEDEX for these patient populations.

8.5 Geriatric Use

Intensive Care Unit Sedation

A total of 729 patients in the clinical studies were 65 years of age and over. A total of 200 patients were 75 years of age and over. In patients greater than 65 years of age, a higher incidence of bradycardia and hypotension was observed following administration of PRECEDEX [see Warnings and Precautions (5.2)]. Therefore, a dose reduction may be considered in patients over 65 years of age [see Dosage and Administration (2.2, 2.3), Clinical Pharmacology (12.3)].

Procedural Sedation

A total of 131 patients in the clinical studies were 65 years of age and over. A total of 47 patients were 75 years of age and over. Hypotension occurred in a higher incidence in PRECEDEX-treated patients 65 years or older (72%) and 75 years or older (74%) as compared to patients <65 years (47%). A reduced loading dose of 0.5 mcg/kg given over 10 minutes is recommended and a reduction in the maintenance infusion should be considered for patients greater than 65 years of age.

8.6 Hepatic Impairment

Since PRECEDEX clearance decreases with increasing severity of hepatic impairment, dose reduction should be considered in patients with impaired hepatic function [see Dosage and Administration (2.2, 2.3), Clinical Pharmacology (12.3)].

9 DRUG ABUSE AND DEPENDENCE

9.1 Controlled Substance

PRECEDEX (dexmedetomidine hydrochloride) is not a controlled substance.

9.3 Dependence

The dependence potential of PRECEDEX has not been studied in humans. However, since studies in rodents and primates have demonstrated that PRECEDEX exhibits pharmacologic actions similar to those of clonidine, it is possible that PRECEDEX may produce a clonidine-like withdrawal syndrome upon abrupt discontinuation [see Warnings and Precautions (5.5)].

10 OVERDOSAGE

The tolerability of PRECEDEX was studied in one study in which healthy adult subjects were administered doses at and above the recommended dose of 0.2 mcg/kg/hr to 0.7 mcg/kg/hr. The maximum blood concentration achieved in this study was approximately 13 times the upper boundary of the therapeutic range. The most notable effects observed in two subjects who achieved the highest doses were first degree atrioventricular block and second-degree heart block. No hemodynamic compromise was noted with the atrioventricular block and the heart block resolved spontaneously within one minute.

Five adult patients received an overdose of PRECEDEX in the intensive care unit sedation studies. Two of these patients had no symptoms reported; one patient received a 2 mcg/kg loading dose over 10 minutes (twice the recommended loading dose) and one patient received a maintenance infusion of 0.8 mcg/kg/hr. Two other patients who received a 2 mcg/kg loading dose over 10 minutes, experienced bradycardia and/or hypotension. One patient who received a loading bolus dose of undiluted PRECEDEX (19.4 mcg/kg), had cardiac arrest from which he was successfully resuscitated.

11 DESCRIPTION

PRECEDEX (dexmedetomidine hydrochloride) injection (100 mcg/mL) is a sterile, nonpyrogenic solution suitable for intravenous infusion following dilution. PRECEDEX (dexmedetomidine hydrochloride) in 0.9% Sodium Chloride Injection (4 mcg/mL) is a sterile, nonpyrogenic ready to use solution suitable for intravenous infusion.

PRECEDEX contains dexmedetomidine hydrochloride as the active pharmaceutical ingredient. Dexmedetomidine hydrochloride is a central alpha2-adrenergic agonist. Dexmedetomidine hydrochloride is the S-enantiomer of medetomidine. Dexmedetomidine hydrochloride chemical name is 1H-Imidazole, 4-[1-(2,3-dimethylphenyl)ethyl]-, monohydrochloride, (S). Dexmedetomidine hydrochloride has a molecular weight of 236.7 and the empirical formula is C13H16N2•HCl and the structural formula is:

Dexmedetomidine hydrochloride is a white or almost white powder that is freely soluble in water and has a pKa of 7.1. Its partition coefficient in-octanol: water at pH 7.4 is 2.89.

PRECEDEX Injection is intended to be used after dilution. It is supplied as a clear, colorless, isotonic solution with a pH between 4.5 to 7.0. Each mL contains 118 mcg of dexmedetomidine hydrochloride (equivalent to 100 mcg or 0.1 mg of dexmedetomidine) and 9 mg of sodium chloride in water for injection. The solution is preservative-free and contains no additives or chemical stabilizers.

PRECEDEX in 0.9% Sodium Chloride Injection is ready to be used. It is supplied as a clear, colorless, isotonic solution with a pH between 4.5 to 8.0. Each mL contains 4.72 mcg of dexmedetomidine hydrochloride (equivalent to 4 mcg or 0.004 mg of dexmedetomidine) and 9 mg sodium chloride in water for injection. The solution is preservative-free and contains no additives or chemical stabilizers.

12 CLINICAL PHARMACOLOGY

12.1 Mechanism of Action

PRECEDEX is a relatively selective centrally acting alpha2-adrenergic agonist with sedative properties. Alpha2 selectivity is observed in animals following slow intravenous infusion of low and medium doses (10–300 mcg/kg). Both alpha1 and alpha2 activity is observed following slow intravenous infusion of high doses (≥1,000 mcg/kg) or with rapid intravenous administration.

12.2 Pharmacodynamics

In a study in healthy adult volunteers (N = 10), respiratory rate and oxygen saturation remained within normal limits and there was no evidence of respiratory depression when PRECEDEX was administered by intravenous infusion at doses within the recommended dose range (0.2 mcg/kg/hr to 0.7 mcg/kg/hr).

12.3 Pharmacokinetics

Following intravenous administration to adults, dexmedetomidine exhibits the following pharmacokinetic parameters: a rapid distribution phase with a distribution half-life (t1/2) of approximately 6 minutes; a terminal elimination half-life (t1/2) of approximately 2 hours; and steady-state volume of distribution (Vss) of approximately 118 liters. Clearance is estimated to be approximately 39 L/h. The mean body weight associated with this clearance estimate was 72 kg.

Dexmedetomidine exhibits linear pharmacokinetics in the dosage range of 0.2 mcg/kg/hr to 0.7 mcg/kg/hr when administered to adults by intravenous infusion for up to 24 hours. Table 10 shows the main pharmacokinetic parameters when PRECEDEX was infused (after appropriate loading doses) at maintenance infusion rates of 0.17 mcg/kg/hr (target plasma concentration of 0.3 ng/mL) for 12 and 24 hours, 0.33 mcg/kg/hr (target plasma concentration of 0.6 ng/mL) for 24 hours, and 0.70 mcg/kg/hr (target plasma concentration of 1.25 ng/mL) for 24 hours.

Table 10: Mean ± SD Pharmacokinetic Parameters in Adults
Parameter | Loading Infusion (min)/Total Infusion Duration (hrs)
Parameter | 10 min/12 hrs | 10 min/24 hrs | 10 min/24 hrs | 35 min/24 hrs
Parameter | Dexmedetomidine Target Plasma Concentration (ng/mL) and Dose (mcg/kg/hr)
Parameter | 0.3/0.17 | 0.3/0.17 | 0.6/0.33 | 1.25/0.70
t1/2 [Presented as harmonic mean and pseudo standard deviation.] , hour | 1.78 ± 0.30 | 2.22 ± 0.59 | 2.23 ± 0.21 | 2.50 ± 0.61
CL, liter/hour | 46.3 ± 8.3 | 43.1 ± 6.5 | 35.3 ± 6.8 | 36.5 ± 7.5
Vss, liter | 88.7 ± 22.9 | 102.4 ± 20.3 | 93.6 ± 17.0 | 99.6 ± 17.8
Avg Css [Mean Css = Average steady-state concentration of dexmedetomidine. The mean Css was calculated based on post-dose sampling from 2.5 to 9 hours samples for 12 hour infusion and post-dose sampling from 2.5 to 18 hours for 24 hour infusions.] , ng/mL | 0.27 ± 0.05 | 0.27 ± 0.05 | 0.67 ± 0.10 | 1.37 ± 0.20
Abbreviations: t1/2 = half‑life, CL = clearance, Vss = steady‑state volume of distribution.

The loading doses for each of the above indicated groups were 0.5, 0.5, 1 and 2.2 mcg/kg, respectively.

Dexmedetomidine pharmacokinetic parameters in adults after PRECEDEX maintenance doses of 0.2 mcg/kg/hr to 1.4 mcg/kg/hr for >24 hours were similar to the pharmacokinetic (PK) parameters after PRECEDEX maintenance dosing for <24 hours in other studies. The values for clearance (CL), volume of distribution (V), and t1/2 were 39.4 L/hr, 152 L, and 2.67 hours, respectively.

Distribution

The steady-state volume of distribution (Vss) of dexmedetomidine was approximately 118 liters. Dexmedetomidine protein binding was assessed in the plasma of normal healthy male and female subjects. The average protein binding was 94% and was constant across the different plasma concentrations tested. Protein binding was similar in males and females. The fraction of PRECEDEX that was bound to plasma proteins was significantly decreased in subjects with hepatic impairment compared to healthy subjects.

The potential for protein binding displacement of dexmedetomidine by fentanyl, ketorolac, theophylline, digoxin and lidocaine was explored in vitro, and negligible changes in the plasma protein binding of PRECEDEX were observed. The potential for protein binding displacement of phenytoin, warfarin, ibuprofen, propranolol, theophylline and digoxin by PRECEDEX was explored in vitro and none of these compounds appeared to be significantly displaced by PRECEDEX.

Elimination

Metabolism

Dexmedetomidine undergoes almost complete biotransformation with very little unchanged dexmedetomidine excreted in urine and feces. Biotransformation involves both direct glucuronidation as well as cytochrome P450 mediated metabolism. The major metabolic pathways of dexmedetomidine are: direct N-glucuronidation to inactive metabolites; aliphatic hydroxylation (mediated primarily by CYP2A6 with a minor role of CYP1A2, CYP2E1, CYP2D6 and CYP2C19) of dexmedetomidine to generate 3-hydroxy-dexmedetomidine, the glucuronide of 3-hydroxy-dexmedetomidine, and 3-carboxy-dexmedetomidine; and N-methylation of dexmedetomidine to generate 3-hydroxy N-methyl-dexmedetomidine, 3-carboxy N-methyl-dexmedetomidine, and dexmedetomidine-N-methyl O-glucuronide.

Excretion

The terminal elimination half-life (t1/2) of dexmedetomidine is approximately 2 hours and clearance is estimated to be approximately 39 L/h. A mass balance study demonstrated that after nine days an average of 95% of the radioactivity, following intravenous administration of radiolabeled dexmedetomidine, was recovered in the urine and 4% in the feces. No unchanged dexmedetomidine was detected in the urine. Approximately 85% of the radioactivity recovered in the urine was excreted within 24 hours after the infusion. Fractionation of the radioactivity excreted in urine demonstrated that products of N-glucuronidation accounted for approximately 34% of the cumulative urinary excretion. In addition, aliphatic hydroxylation of parent drug to form 3-hydroxy-dexmedetomidine, the glucuronide of 3-hydroxy-dexmedetomidine, and 3-carboxylic acid-dexmedetomidine together represented approximately 14% of the dose in urine. N-methylation of dexmedetomidine to form 3-hydroxy N-methyl dexmedetomidine, 3-carboxy N-methyl dexmedetomidine, and N-methyl O-glucuronide dexmedetomidine accounted for approximately 18% of the dose in urine. The N-Methyl metabolite itself was a minor circulating component and was undetected in urine. Approximately 28% of the urinary metabolites have not been identified.

Specific Populations

Male and Female Patients

There was no observed difference in PRECEDEX pharmacokinetics due to sex.

Geriatric Patients

The pharmacokinetic profile of PRECEDEX was not altered by age. There were no differences in the pharmacokinetics of PRECEDEX in young (18–40 years), middle age (41–65 years), and elderly (>65 years) subjects.

Pediatric Patients

A population PK analysis was conducted with data collected from mechanically ventilated pediatric patients less than 17 years of age from 4 clinical studies. A linear 2-compartment model was found to best characterize the pooled dexmedetomidine concentration data. Mean PK parameters for each age group are summarized in Table 11.

Table 11: Geometric Mean Point Estimates and 95% Confidence Intervals of PK Parameters by Pediatric Age Group
Age Group | N | CL (L/h) | Vc (L)
1 to less than 6 months | 14 | 6.94 (5.46, 8.81) | 4.34 (3.25, 5.81)
6 to less than 12 months | 15 | 8.15 (7.01, 9.47) | 7.29 (5.57, 9.53)
12 to less than 24 months | 13 | 10.76 (9.09, 12.74) | 7.35 (5.59, 9.67)
2 to less than 6 years | 26 | 15.89 (14.00, 18.04) | 13.78 (10.66, 17.83)
6 to less than 17 years | 28 | 24.45 (19.34, 30.92) | 24.47 (17.06, 35.10)
Abbreviations: CL = plasma clearance, Vc = volume of the central compartment.

Patients with Hepatic Impairment

In adult subjects with varying degrees of hepatic impairment (Child-Pugh Class A, B, or C), clearance values for PRECEDEX were lower than in healthy subjects. The mean clearance values for patients with mild, moderate, and severe hepatic impairment were 74%, 64% and 53% of those observed in the normal healthy adult subjects, respectively. Mean clearances for free drug were 59%, 51% and 32% of those observed in the normal healthy adult subjects, respectively.

Although PRECEDEX is dosed to effect, it may be necessary to consider dose reduction in subjects with hepatic impairment [see Dosage and Administration (2.2), Warnings and Precautions (5.8)].

Patients with Renal Impairment

Dexmedetomidine pharmacokinetics (Cmax, Tmax, AUC, t1/2, CL, and Vss) were not significantly different in patients with severe renal impairment (creatinine clearance: <30 mL/min) compared to healthy subjects.

Drug Interaction Studies

In vitro studies: In vitro studies in human liver microsomes demonstrated no evidence of cytochrome P450 mediated drug interactions that are likely to be of clinical relevance.

13 NONCLINICAL TOXICOLOGY

13.1 Carcinogenesis, Mutagenesis, Impairment of Fertility

Carcinogenesis

Animal carcinogenicity studies have not been performed with dexmedetomidine.

Mutagenesis

Dexmedetomidine was not mutagenic in vitro, in either the bacterial reverse mutation assay (E. coli and Salmonella typhimurium) or the mammalian cell forward mutation assay (mouse lymphoma). Dexmedetomidine was clastogenic in the in vitro human lymphocyte chromosome aberration test with, but not without, rat S9 metabolic activation. In contrast, dexmedetomidine was not clastogenic in the in vitro human lymphocyte chromosome aberration test with or without human S9 metabolic activation. Although dexmedetomidine was clastogenic in an in vivo mouse micronucleus test in NMRI mice, there was no evidence of clastogenicity in CD-1 mice.

Impairment of Fertility

Fertility in male or female rats was not affected after daily subcutaneous injections of dexmedetomidine at doses up to 54 mcg/kg (less than the maximum recommended human intravenous dose on a mcg/m^2 basis) administered from 10 weeks prior to mating in males, and 3 weeks prior to mating and during mating in females.

13.2 Animal Toxicology and/or Pharmacology

There were no differences in the adrenocorticotropic hormone (ACTH)-stimulated cortisol response in dogs following a single-dose of dexmedetomidine compared to saline control. However, after continuous subcutaneous infusions of dexmedetomidine at 3 mcg/kg/hr and 10 mcg/kg/hr for one week in dogs (exposures estimated to be within the clinical range), the ACTH-stimulated cortisol response was diminished by approximately 27% and 40%, respectively, compared to saline-treated control animals indicating a dose‑dependent adrenal suppression.

14 CLINICAL STUDIES

The safety and efficacy of PRECEDEX has been evaluated in four randomized, double-blind, placebo-controlled multicenter clinical trials in 1,185 adult patients.

14.1 Intensive Care Unit Sedation

Two randomized, double-blind, parallel-group, placebo-controlled multicenter clinical trials included 754 adult patients being treated in a surgical intensive care unit. All patients were initially intubated and received mechanical ventilation. These trials evaluated the sedative properties of PRECEDEX by comparing the amount of rescue medication (midazolam in one trial and propofol in the second) required to achieve a specified level of sedation (using the standardized Ramsay Sedation Scale) between PRECEDEX and placebo from onset of treatment to extubation or to a total treatment duration of 24 hours. The Ramsay Level of Sedation Scale is displayed in Table 12.

Table 12: Ramsay Level of Sedation Scale
Clinical Score | Level of Sedation Achieved
6 | Asleep, no response
5 | Asleep, sluggish response to light glabellar tap or loud auditory stimulus
4 | Asleep, but with brisk response to light glabellar tap or loud auditory stimulus
3 | Patient responds to commands
2 | Patient cooperative, oriented, and tranquil
1 | Patient anxious, agitated, or restless

In the first study, 175 adult patients were randomized to receive placebo and 178 to receive PRECEDEX by intravenous infusion at a dose of 0.4 mcg/kg/hr (with allowed adjustment between 0.2 mcg/kg/hr and 0.7 mcg/kg/hr) following an initial loading infusion of one mcg/kg intravenous over 10 minutes. The study drug infusion rate was adjusted to maintain a Ramsay sedation score of ≥3. Patients were allowed to receive "rescue" midazolam as needed to augment the study drug infusion. In addition, morphine sulfate was administered for pain as needed. The primary outcome measure for this study was the total amount of rescue medication (midazolam) needed to maintain sedation as specified while intubated. Patients randomized to placebo received significantly more midazolam than patients randomized to PRECEDEX (see Table 13).

A second prospective primary analysis assessed the sedative effects of PRECEDEX by comparing the percentage of adult patients who achieved a Ramsay sedation score of ≥3 during intubation without the use of additional rescue medication. A significantly greater percentage of adult patients in the PRECEDEX group maintained a Ramsay sedation score of ≥3 without receiving any midazolam rescue compared to the placebo group (see Table 13).

Table 13: Midazolam Use as Rescue Medication During Intubation (ITT) Study One
 | Placebo (N = 175) | PRECEDEX (N = 178) | p-value
Mean Total Dose (mg) of Midazolam | 19 mg | 5 mg | 0.0011 [ANOVA model with treatment center.]
Standard deviation | 53 mg | 19 mg
Categorized Midazolam Use
0 mg | 43 (25%) | 108 (61%) | <0.001 [Chi-square.]
0–4 mg | 34 (19%) | 36 (20%)
>4 mg | 98 (56%) | 34 (19%)
ITT (intent-to-treat) population includes all randomized patients.

A prospective secondary analysis assessed the dose of morphine sulfate administered to adult patients in the PRECEDEX and placebo groups. On average, PRECEDEX-treated patients received less morphine sulfate for pain than placebo‑treated patients (0.47 versus 0.83 mg/h). In addition, 44% (79 of 178 patients) of PRECEDEX patients received no morphine sulfate for pain versus 19% (33 of 175 patients) in the placebo group.

In a second study, 198 adult patients were randomized to receive placebo and 203 to receive PRECEDEX by intravenous infusion at a dose of 0.4 mcg/kg/hr (with allowed adjustment between 0.2 mcg/kg/hr and 0.7 mcg/kg/hr) following an initial loading infusion of one mcg/kg intravenous over 10 minutes. The study drug infusion was adjusted to maintain a Ramsay sedation score of ≥3. Patients were allowed to receive "rescue" propofol as needed to augment the study drug infusion. In addition, morphine sulfate was administered as needed for pain. The primary outcome measure for this study was the total amount of rescue medication (propofol) needed to maintain sedation as specified while intubated.

Adult patients randomized to placebo received significantly more propofol than adult patients randomized to PRECEDEX (see Table 14).

A significantly greater percentage of adult patients in the PRECEDEX group compared to the placebo group maintained a Ramsay sedation score of ≥3 without receiving any propofol rescue (see Table 14).

Table 14: Propofol Use as Rescue Medication During Intubation (ITT) Study Two
 | Placebo (N = 198) | PRECEDEX (N = 203) | p-value
Mean Total Dose (mg) of Propofol | 513 mg | 72 mg | <0.0001 [ANOVA model with treatment center.]
Standard deviation | 782 mg | 249 mg
Categorized Propofol Use
0 mg | 47 (24%) | 122 (60%) | <0.001 [Chi-square.]
0–50 mg | 30 (15%) | 43 (21%)
>50 mg | 121 (61%) | 38 (19%)

A prospective secondary analysis assessed the dose of morphine sulfate administered to adult patients in the PRECEDEX and placebo groups. On average, PRECEDEX-treated patients received less morphine sulfate for pain than placebo-treated patients (0.43 versus 0.89 mg/h). In addition, 41% (83 of 203 patients) of PRECEDEX patients received no morphine sulfate for pain versus 15% (30 of 198 patients) in the placebo group.

In a controlled clinical trial, PRECEDEX was compared to midazolam for ICU sedation exceeding 24 hours duration. PRECEDEX was not shown to be superior to midazolam for the primary efficacy endpoint, the percent of time patients were adequately sedated (81% versus 81%). In addition, administration of PRECEDEX for longer than 24 hours was associated with tolerance, tachyphylaxis, and a dose-related increase in adverse events [see Adverse Reactions (6.1)].

14.2 Procedural Sedation

Adult Patients

The safety and efficacy of PRECEDEX for sedation of non-intubated adult patients prior to and/or during surgical and other procedures was evaluated in two randomized, double-blind, placebo-controlled multicenter clinical trials. Study 1 evaluated the sedative properties of PRECEDEX in adult patients having a variety of elective surgeries/procedures performed under monitored anesthesia care. Study 2 evaluated PRECEDEX in adult patients undergoing awake fiberoptic intubation prior to a surgical or diagnostic procedure.

In Study 1, the sedative properties of PRECEDEX were evaluated by comparing the percent of adult patients not requiring rescue midazolam to achieve a specified level of sedation using the standardized Observer's Assessment of Alertness/Sedation Scale (see Table 15).

Table 15: Observer's Assessment of Alertness/Sedation
Assessment Categories
Responsiveness | Speech | Facial Expression | Eyes | Composite Score
Responds readily to name spoken in normal tone | Normal | Normal | Clear, no ptosis | 5 (alert)
Lethargic response to name spoken in normal tone | Mild slowing or thickening | Mild relaxation | Glazed or mild ptosis (less than half the eye) | 4
Responds only after name is called loudly and/or repeatedly | Slurring or prominent slowing | Marked relaxation (slack jaw) | Glazed and marked ptosis (half the eye or more) | 3
Responds only after mild prodding or shaking | Few recognizable words | – | – | 2
Does not respond to mild prodding or shaking | – | – | – | 1 (deep sleep)

Adult patients were randomized to receive a loading infusion of either PRECEDEX 1 mcg/kg, PRECEDEX 0.5 mcg/kg, or placebo (normal saline) given over 10 minutes and followed by a maintenance infusion started at 0.6 mcg/kg/hr. The maintenance infusion of study drug could be titrated from 0.2 mcg/kg/hr to 1 mcg/kg/hr to achieve the targeted sedation score (Observer's Assessment of Alertness/Sedation Scale ≤4). Adult patients were allowed to receive rescue midazolam as needed to achieve and/or maintain an Observer's Assessment of Alertness/Sedation Scale ≤4. After achieving the desired level of sedation, a local or regional anesthetic block was performed. Demographic characteristics were similar between the PRECEDEX and comparator groups. Efficacy results showed that PRECEDEX was more effective than the comparator group when used to sedate non‑intubated patients requiring monitored anesthesia care during surgical and other procedures (see Table 15).

In Study 2, the sedative properties of PRECEDEX were evaluated by comparing the percent of adult patients requiring rescue midazolam to achieve or maintain a specified level of sedation using the Ramsay Sedation Scale score ≥2 (see Table 12). Adult patients were randomized to receive a loading infusion of PRECEDEX 1 mcg/kg or placebo (normal saline) given over 10 minutes and followed by a fixed maintenance infusion of 0.7 mcg/kg/hr. After achieving the desired level of sedation, topicalization of the airway occurred. Adult patients were allowed to receive rescue midazolam as needed to achieve and/or maintain a Ramsay Sedation Scale ≥2. Demographic characteristics were similar between the PRECEDEX and comparator groups. For efficacy results see Table 16.

Table 16: Key Efficacy Results of Adult Procedural Sedation Studies
Study | Loading Infusion Treatment Arm | Number of Patients Enrolled [Based on ITT population defined as all randomized and treated patients.] | % Not Requiring Midazolam Rescue | Confidence [Normal approximation to the binomial with continuity correction.] Interval on the Difference vs. Placebo | Mean (SD) Total Dose (mg) of Rescue Midazolam Required | Confidence Intervals of the Mean Rescue Dose
Study 1 | Dexmedetomidine 0.5 mcg/kg | 134 | 40 | 37 (27, 48) | 1.4 (1.7) | -2.7 (-3.4, -2.0)
Study 1 | Dexmedetomidine 1 mcg/kg | 129 | 54 | 51 (40, 62) | 0.9 (1.5) | -3.1 (-3.8, -2.5)
Study 1 | Placebo | 63 | 3 | – | 4.1 (3.0) | –
Study 2 | Dexmedetomidine 1 mcg/kg | 55 | 53 | 39 (20, 57) | 1.1 (1.5) | -1.8 (-2.7, -0.9)
Study 2 | Placebo | 50 | 14 | – | 2.9 (3.0) | –

Pediatric Patients

The safety and efficacy of PRECEDEX for sedation of non-intubated pediatric patients aged 1 month to less than 17 years undergoing MRI scans was evaluated in one randomized, double-blind, dose-ranging, dose‑controlled multicenter clinical trial utilizing 3 different PRECEDEX dosages. The sedative properties of PRECEDEX were evaluated by age group and by the percent of pediatric patients at the high dose level versus the low dose level who did not require concomitant propofol to complete the MRI scan.

A total of 122 pediatric patients were randomized to the PRECEDEX low dose group (42 of 122), the middle dose group (42 of 122) or the high dose treatment group (38 of 122). All patients received a PRECEDEX loading dose infusion over 10 minutes followed by a maintenance infusion for the duration of the MRI scan (Table 17). If an adequate level of sedation was not achieved within 5 minutes after the start of the PRECEDEX maintenance infusion, patients could receive concomitant propofol as needed based on clinical judgment to achieve and/or maintain adequate sedation.

Table 17: PRECEDEX Loading and Maintenance Doses
 | High Dose |  | Middle Dose |  | Low Dose
Age | Loading Dose; (10 min) | Maintenance Dose | Loading Dose; (10 min) | Maintenance Dose | Loading Dose; (10 min) | Maintenance Dose
1 month to less than 2 years | 1.5 mcg/kg | 1.5 mcg/kg/h | 1 mcg/kg | 1 mcg/kg/h | 0.5 mcg/kg | 0.5 mcg/kg/h
2 to less than 17 years | 2 mcg/kg | 1.5 mcg/kg/h | 1.2 mcg /kg | 1 mcg/kg/h | 0.5 mcg/kg | 0.5 mcg kg/h

The primary efficacy results from this pediatric procedural sedation study are summarized in Table 18. In the combined age group, the percent of pediatric patients not requiring concomitant propofol was 14.3% (6/42) in the low dose group and 63.2% (24/38) in the high dose group. The percentage of patients at the PRECEDEX high dose who completed the MRI without concomitant propofol was statistically greater than the percentage in the PRECEDEX low dose group (p<0.001).

Table 18: Percent of Pediatric Patients not Requiring Concomitant Propofol by Age Group and Overall
Age Group |  | High Dose | Middle Dose | Low Dose | High Dose vs Low Dose
 |  | n (%); 95% CI [Exact 95% CI of proportion of subjects not requiring propofol in each dose level.] | n (%); 95% CI | n (%); 95% CI | Odds Ratio; 95% CI [p-values; CI is confidence interval of odds ratio.] | p-value
1 month to less than 2 years | N=59 | 9/18 (50.0%); (0.26, 0.74) | 2/21 (9.5%); (0.01, 0.30) | 2/20 (15.0%); (0.03, 0.38) | 0.18 (0.04, 0.82) | 0.022
2 to less than 17 years | N=63 | 15/20 (75.0%); (0.51, 0.91) | 13/21 (61.9%); (0.38, 0.82) | 3/22 (13.6%); (0.03, 0.35) | 0.05 (0.01, 0.26) | <0.001
Overall | N=122 | 24/38 (63.2%); (0.46, 0.78) | 15/42 (35.7%); (0.22, 0.52) | 6/42 (14.3%); (0.05, 0.29) | 0.10 (0.03, 0.29) | <0.001

Secondarily, the sedative properties were also evaluated by examining the percent of time at a target sedation score using the Pediatric Sedation State Scale (PSSS). The PSSS is a validated 6-point scale specifically designed for evaluating pediatric patients undergoing sedation for diagnostic and therapeutic procedures. The PSSS measures the effectiveness and quality of procedural sedation in children. The target sedation level was indicated by a PSSS score of 2 (i.e., patient is quiet [asleep or awake], not moving during procedure, has no frown [or brow furrow] indicating pain or anxiety and no verbalization of any complaint).

In the PRECEDEX high dose group, pediatric patients in both the combined and individual age group were at the target sedation rating scale score (PSSS of 2) for a mean >87% of the time during the PRECEDEX maintenance infusion. In both the combined and individual age group, an increase in the percentage of time at the target sedation rating scale score (PSSS of 2) was observed with increasing PRECEDEX dosage.

16 HOW SUPPLIED/STORAGE AND HANDLING

STORAGE AND HANDLING

Store at 20°C to 25°C (68°F to 77°F); excursions permitted between 15°C to 30°C (59°F to 86°F). [See USP Controlled Room Temperature.]

Do not use if product is discolored or if precipitate matter is present.

PRECEDEX (dexmedetomidine hydrochloride) injection 200 mcg/2 mL (100 mcg/mL) is clear and colorless. The strength is based on the dexmedetomidine base. Discard unused portion.

Unit of Sale | Concentration
NDC 0409-1638-02; Tray of 25 single-dose clear glass vials | 200 mcg/2 mL; (100 mcg/mL)

PRECEDEX (dexmedetomidine hydrochloride in 0.9% Sodium Chloride) injection (4 mcg/mL) is clear and colorless. The strength is based on the dexmedetomidine base. Discard unused portion.

Unit of Sale | Concentration
NDC 0409-1660-20; Carton of 10 single-dose clear glass vials | 80 mcg/20 mL; (4 mcg/mL)
NDC 0409-1660-50; Tray of 20 single-dose clear glass bottles | 200 mcg/50 mL; (4 mcg/mL)
NDC 0409-1660-10; Tray of 10 single-dose clear glass bottles | 400 mcg/100 mL; (4 mcg/mL)
NDC 0409-1596-10; Case of 10 cartons containing 1 single-dose clear glass bottle | 400 mcg/100 mL; (4 mcg/mL)
NDC 0409-1434-01; Carton containing 1 single-dose clear glass bottle | 1,000 mcg/250 mL; (4 mcg/mL)
NDC 0409-7838-24; Case of 24 single-dose flexible containers | 200 mcg/50 mL; (4 mcg/mL)
NDC 0409-7853-24; Case of 24 single-dose flexible containers | 400 mcg/100 mL; (4 mcg/mL)
NDC 0409-7875-12; Case of 12 single-dose flexible containers | 1,000 mcg/250 mL; (4 mcg/mL)

17 PATIENT COUNSELING INFORMATION

PRECEDEX is indicated for short-term intravenous sedation. Dosage must be individualized and titrated to the desired clinical effect. Blood pressure, heart rate and oxygen levels will be monitored both continuously during the infusion of PRECEDEX and as clinically appropriate after discontinuation.

- When PRECEDEX is infused for more than 6 hours, patients should be informed to report nervousness, agitation, and headaches that may occur for up to 48 hours.
- Additionally, patients should be informed to report symptoms that may occur within 48 hours after the administration of PRECEDEX such as: weakness, confusion, excessive sweating, weight loss, abdominal pain, salt cravings, diarrhea, constipation, dizziness or light-headedness.
- Advise breastfeeding mothers who were exposed to PRECEDEX to monitor breastfed neonates for irritability [see Use in Specific Populations (8.2)].

Distributed by Hospira, Inc. Lake Forest, IL 60045

LAB-1346-6.0

PRINCIPAL DISPLAY PANEL - 50 mL Bottle Label

50 mL
Rx only
NDC 0409-1660-55

Single-dose bottle. Discard unused portion.

Precedex™
Dexmedetomidine HCl
in 0.9% Sodium Chloride
Injection

200 mcg/50 mL
(4 mcg/mL)

For Intravenous Use

PRINCIPAL DISPLAY PANEL - 50 mL Bottle Tray

20 Units X 50 mL
Rx only
NDC 0409-1660-50
Contains 20 of NDC 0409-1660-55

Single-dose bottle. Discard unused portion.

Precedex™
Dexmedetomidine HCl
in 0.9% Sodium Chloride Injection

200 mcg/50 mL
(4 mcg/mL)

For Intravenous Use

Hospira

PRINCIPAL DISPLAY PANEL - 100 mL Bottle Label

100 mL
Rx only
NDC 0409-1660-35

Single-dose bottle. Discard unused portion.

Precedex™
Dexmedetomidine HCl
in 0.9% Sodium Chloride
Injection

400 mcg/100 mL
(4 mcg/mL)

For Intravenous Use

PRINCIPAL DISPLAY PANEL - 100 mL Bottle Tray

10 Units X 100 mL
Rx only
NDC 0409-1660-10
Contains 10 of NDC 0409-1660-35

Single-dose bottle. Discard unused portion.

Precedex™
Dexmedetomidine HCl in 0.9% Sodium Chloride Injection

400 mcg/100 mL
(4 mcg/mL)

For Intravenous Use
Hospira

PRINCIPAL DISPLAY PANEL - 20 mL Vial Label

20 mL
NDC 0409-1660-22

Single-dose vial. Discard unused portion.

Precedex™
Dexmedetomidine HCl
in 0.9% Sodium Chloride Injection

80 mcg/20 mL
(4 mcg/mL)

Distributed by Hospira, Inc., Lake Forest, IL 60045 USA

PRINCIPAL DISPLAY PANEL - 20 mL Vial Carton

10 units x 20 mL
Rx only
NDC 0409-1660-20
Contains 10 of NDC 0409-1660-22

Single-dose vial. Discard unused portion.

Precedex™
Dexmedetomidine HCl in 0.9% Sodium Chloride Injection

80 mcg/20 mL
(4 mcg/mL)

Hospira

For Intravenous Use

PRINCIPAL DISPLAY PANEL - 2 mL Vial Label

2 mL NDC 0409-1638-32

Precedex™
DEXMEDETOMIDINE
HCl INJECTION
Rx only

200 mcg/2 mL
(100 mcg/mL)

For Intravenous use.
MUST BE DILUTED

Dist. by Hospira, Inc.,
Lake Forest, IL 60045 USA

RL–7616

##–###–AA
DMMMYYYY

PRINCIPAL DISPLAY PANEL - 2 mL Vial Tray

2 mL Single-dose Fliptop Vials
Preservative-Free
NDC 0409-1638-02
Contains 25 of NDC 0409-1638-32

Precedex™
DEXMEDETOMIDINE HCl INJECTION
Rx only

200 mcg/2 mL
(100 mcg/mL)

For Intravenous use.
MUST BE DILUTED

Hospira

PRINCIPAL DISPLAY PANEL - 250 mL Bottle Label

250 mL
Rx only
NDC 0409-1434-01

Single-dose bottle. Discard unused portion.

Precedex™
Dexmedetomidine HCl
in 0.9% Sodium
Chloride Injection

1,000 mcg/250 mL
(4 mcg/mL)

For Intravenous Use

PRINCIPAL DISPLAY PANEL - 250 mL Bottle Carton

NDC 0409-1434-01

1 Unit X 250 mL
Rx only

Single-dose bottle.
Discard unused portion.

Precedex™
Dexmedetomidine HCl
in 0.9% Sodium Chloride
Injection

1,000 mcg/250 mL
(4 mcg/mL)

For Intravenous Use

Hospira

PRINCIPAL DISPLAY PANEL – 100 mL Bottle Label - 1596

100 mL
Rx only
NDC 0409-1596-01

Single-dose bottle. Discard unused portion.

PrecedexTM
Dexmedetomidine HCl
in 0.9% Sodium Chloride
Injection

400 mcg/100 mL
(4 mcg/mL)

For Intravenous Use

PRINCIPAL DISPLAY PANEL – 100 mL Bottle Carton - 1596

NDC 0409-1596-01

Rx only

100 mL Single-dose bottle.
Discard unused portion.

PrecedexTM
Dexmedetomidine HCl
in 0.9% Sodium Chloride
Injection

400 mcg/100 mL
(4 mcg/mL)

For Intravenous Use

Hospira

PRINCIPAL DISPLAY PANEL – 50 mL Bag - 7838

50 mL Single-dose. Discard unused portion.
NDC 0409-7838-01
PrecedexTM
Dexmedetomidine HCl
in 0.9% Sodium Chloride
Injection
Rx only
200 mcg/50 mL (4mcg/mL)
For Intravenous Infusion Each mL contains 4 mcg of dexmedetomidine
provided as 4.72 mcg dexmedetomidine HCl and 9 mg of sodium chloride in
water for injection.
Recommended Dosage: See prescribing information. Store at 20˚C to 25˚C
(68˚F to 77˚F). [See USP Controlled Room Temperature.] Do not freeze.
This product is not made with natural rubber latex.

Preservative-Free.
1000072255
Distributed by Hospira, Inc.
Lake Forest, IL 60045 USA
Hospira

PRINCIPAL DISPLAY PANEL – 100 mL Bag - 7853

100 mL Single-dose. Discard unused portion.
NDC 0409-7853-01
PrecedexTM
Dexmedetomidine HCl
in 0.9% Sodium Chloride
Injection
Rx only
400 mcg/100 mL (4 mcg/mL)
For Intravenous Infusion Each mL contains 4 mcg of dexmedetomidine provided
as 4.72 mcg dexmedetomidine HCl and 9 mg of sodium chloride in water for
injection.
Recommended Dosage: See prescribing information. Storage at 20ºC to 25ºC
(68ºF to 77ºF).[See USP Controlled Room Temperature.] Do not Freeze.
This product is not made with natural rubber latex.
Preservative-Free.
1000072256
Distributed by Hospira, Inc.
Lake Forest, IL 60045 USA
Hospira

PRINCIPAL DISPLAY PANEL – 250 mL Bag - 7875

250 mL Single-dose. Discard unused portion.
NDC 0409-7875-01
PrecedexTM
Dexmedetomidine HCl
in 0.9% Sodium Chloride
Injection
1,000 mcg/250 mL (4 mcg/mL)
For Intravenous Infusion Each mL contains 4 mcg of dexmedetomidine provided
as 4.72 mcg dexmedetomidine HCl and 9 mg of sodium chloride in water for
injection.
Recommended Dosage: See prescribing information. Store at
20˚C to 25˚C (68˚F to 77˚F). [See USP Controlled Room

Temperature.] Do not freeze.
This product is not made with natural
rubber latex.
Preservative-Free.
Rx only
1000072257
Distributed by Hospira, Inc.
Lake Forest, IL 60045 USA
Hospira